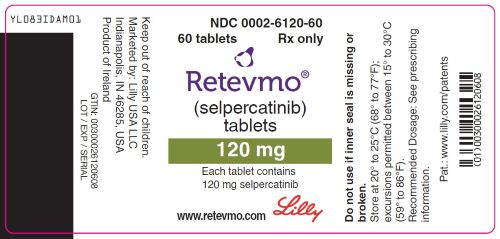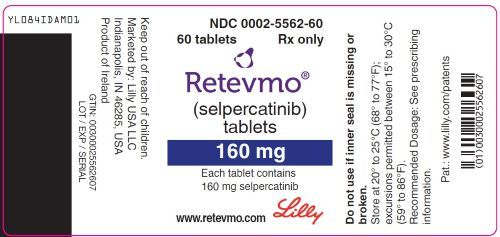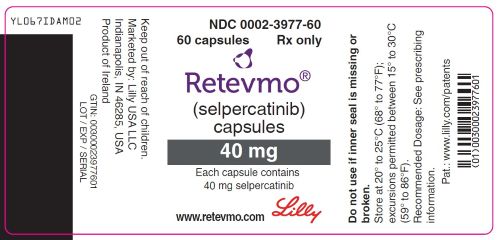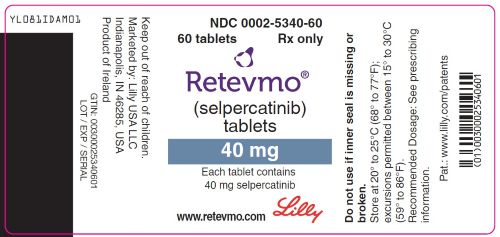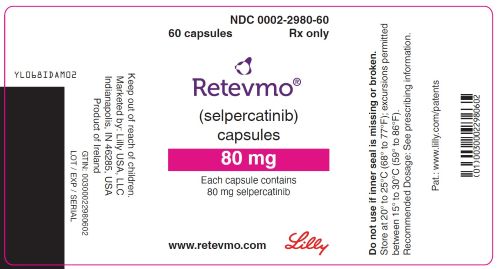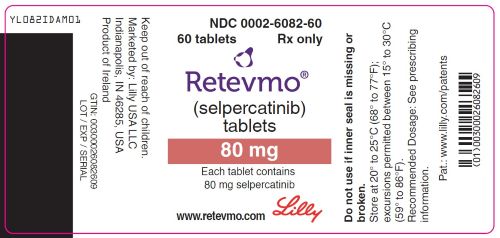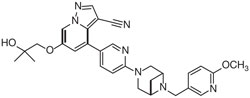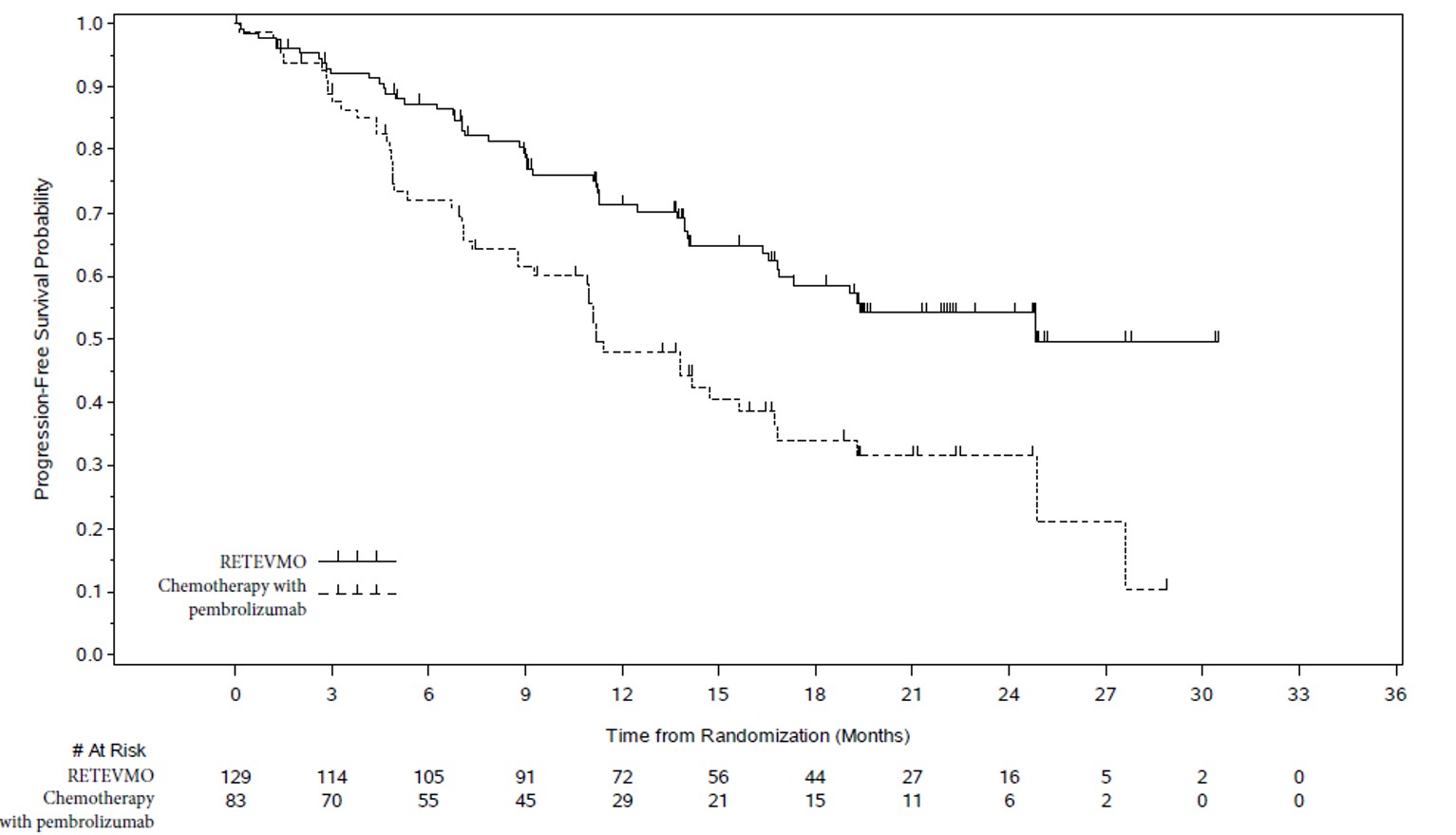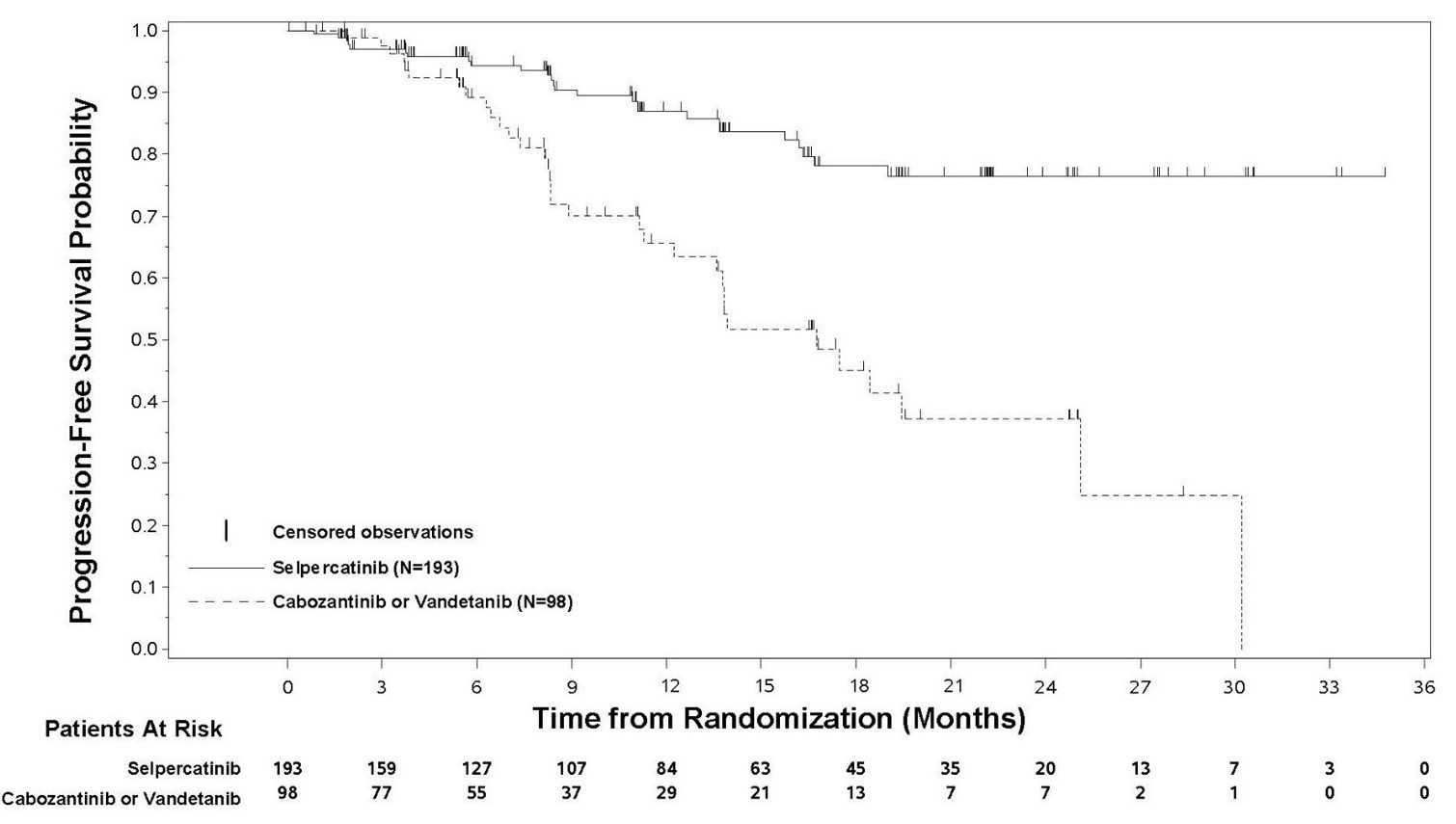 DRUG LABEL: RETEVMO
NDC: 0002-3977 | Form: CAPSULE
Manufacturer: Eli Lilly and Company
Category: prescription | Type: HUMAN PRESCRIPTION DRUG LABEL
Date: 20251120

ACTIVE INGREDIENTS: selpercatinib 40 mg/1 1
INACTIVE INGREDIENTS: microcrystalline cellulose; silicon dioxide; gelatin, unspecified; titanium dioxide; ferrosoferric oxide; shellac; alcohol; isopropyl alcohol; butyl alcohol; propylene glycol; water; ammonia; potassium hydroxide

HIGHLIGHTS OF PRESCRIBING INFORMATION

These highlights do not include all the information needed to use RETEVMO safely and effectively. See full prescribing information for RETEVMO.
RETEVMO® (selpercatinib) capsules, for oral use
RETEVMO® (selpercatinib) tablets, for oral use
Initial U.S. Approval: 2020

RECENT MAJOR CHANGES

Dosage and Administration (2.8) | 11/2025
Warnings and Precautions (5.6) | 11/2025

1 INDICATIONS AND USAGE

RETEVMO® is a kinase inhibitor indicated for the treatment of:

- Adult patients with locally advanced or metastatic non-small cell lung cancer (NSCLC) with a rearranged during transfection (RET) gene fusion, as detected by an FDA-approved test (1.1)
- Adult and pediatric patients 2 years of age and older with advanced or metastatic medullary thyroid cancer (MTC) with a RET mutation, as detected by an FDA-approved test, who require systemic therapy (1.2)
- Adult and pediatric patients 2 years of age and older with advanced or metastatic thyroid cancer with a RET gene fusion, as detected by an FDA-approved test, who require systemic therapy and who are radioactive iodine-refractory (if radioactive iodine is appropriate) (1.3)
- Adult and pediatric patients 2 years of age and older with locally advanced or metastatic solid tumors with a RET gene fusion, as detected by an FDA-approved test, that have progressed on or following prior systemic treatment or who have no satisfactory alternative treatment options^1 (1.4)

^1 This indication is approved under accelerated approval based on overall response rate and duration of response. Continued approval for this indication may be contingent upon verification and description of clinical benefit in confirmatory trial(s).

2 DOSAGE AND ADMINISTRATION

- Select patients for treatment with RETEVMO based on the presence of a RET gene fusion (NSCLC, thyroid, or other solid tumors) or specific RET gene mutation (MTC). (2.1, 14)
- Adult and adolescent patients 12 years of age or older:
  the recommended dosage is based on weight (2.3):
  - Less than 50 kg: 120 mg orally twice daily
  - 50 kg or greater: 160 mg orally twice daily
- Pediatric patients 2 to less than 12 years of age:
  the recommended dosage is based on body surface area (2.3):
  - 0.33 m^2 to 0.65 m^2: 40 mg orally three times daily
  - 0.66 m^2 to 1.08 m^2: 80 mg orally twice daily
  - 1.09 m^2 to 1.52 m^2: 120 mg orally twice daily
  - ≥1.53 m^2: 160 mg orally twice daily
- For patients who cannot swallow, disperse 40 mg RETEVMO tablets and administer orally or via gastrostomy or nasogastric tube (2.8)
- Only RETEVMO 40 mg tablets may be used to create the dispersion (2.2)
- Reduce RETEVMO dose in patients with severe hepatic impairment. (2.7, 8.7)

3 DOSAGE FORMS AND STRENGTHS

- Capsules: 40 mg, 80 mg. (3)
- Tablets: 40 mg, 80 mg, 120 mg, 160 mg. (3)

4 CONTRAINDICATIONS

None. (4)

5 WARNINGS AND PRECAUTIONS

- Hepatotoxicity: Monitor ALT and AST prior to initiating RETEVMO, every 2 weeks during the first 3 months, then monthly thereafter and as clinically indicated. Withhold, reduce the dose, or permanently discontinue RETEVMO based on severity. (2.5, 5.1)
- Interstitial Lung Disease (ILD)/Pneumonitis: Monitor for new or worsening pulmonary symptoms. Withhold, reduce the dose or permanently discontinue RETEVMO based on severity. (2.5, 5.2)
- Hypertension: Do not initiate RETEVMO in patients with uncontrolled hypertension. Optimize blood pressure (BP) prior to initiating RETEVMO. Monitor BP after 1 week, at least monthly thereafter and as clinically indicated. Withhold, reduce the dose, or permanently discontinue RETEVMO based on severity. (2.5, 5.3)
- QT Interval Prolongation: Monitor patients who are at significant risk of developing QTc prolongation. Assess QT interval, electrolytes and TSH at baseline and periodically during treatment. Monitor QT interval more frequently when RETEVMO is concomitantly administered with strong and moderate CYP3A inhibitors or drugs known to prolong QTc interval. Withhold and reduce the dose or permanently discontinue RETEVMO based on severity. (2.5, 5.4)
- Hemorrhagic Events: Permanently discontinue RETEVMO in patients with severe or life-threatening hemorrhage. (2.5, 5.5)
- Hypersensitivity: Withhold RETEVMO and initiate corticosteroids. Upon resolution, resume at a reduced dose and increase dose by 1 dose level each week until reaching the dose taken prior to onset of hypersensitivity. Continue steroids until patient reaches target dose and then taper. (2.5, 5.6)
- Tumor Lysis Syndrome: Closely monitor patients at risk and treat as clinically indicated. (5.7)
- Risk of Impaired Wound Healing: Withhold RETEVMO for at least 7 days prior to elective surgery. Do not administer for at least 2 weeks following major surgery and until adequate wound healing. The safety of resumption of RETEVMO after resolution of wound healing complications has not been established. (5.8)
- Hypothyroidism: Monitor thyroid function before treatment with RETEVMO and periodically during treatment. Withhold until clinically stable or permanently discontinue based on severity. (5.9)
- Embryo-Fetal Toxicity: Can cause fetal harm. Advise females of reproductive potential of the possible risk to a fetus and to use effective contraception. (5.10, 8.1, 8.3)
- Slipped Capital Femoral Epiphysis/Slipped Upper Femoral Epiphysis (SCFE/SUFE) in Pediatric Patients: Monitor patients for symptoms indicative of SCFE/SUFE and treat as medically and surgically appropriate (5.11, 6.1)

6 ADVERSE REACTIONS

The most common adverse reactions (≥25%) include:

- Adult patients with solid tumors: edema, diarrhea, fatigue, dry mouth, hypertension, abdominal pain, constipation, rash, nausea, and headache. (6)
- Pediatric patients with solid tumors: musculoskeletal pain, diarrhea, nausea, hemorrhage, pyrexia, abdominal pain, headache, vomiting, fatigue, cough, rash, coronavirus infection, upper respiratory tract infection, and edema. (6)

The most common Grade 3 or 4 laboratory abnormalities (≥5%) include:

- Adult patients with solid tumors: decreased lymphocytes, increased alanine aminotransferase (ALT), increased aspartate aminotransferase (AST), decreased sodium, and decreased calcium. (6)
- Pediatric patients with solid tumors: decreased lymphocytes, decreased calcium, decreased hemoglobin, decreased neutrophils, increased alanine aminotransferase, decreased magnesium, and decreased potassium. (6)

To report SUSPECTED ADVERSE REACTIONS, contact Eli Lilly and Company at 1-800-LillyRx (1-800-545-5979) or FDA at 1-800-FDA-1088 or www.fda.gov/medwatch.

7 DRUG INTERACTIONS

- Acid-Reducing Agents: Avoid coadministration. If coadministration cannot be avoided, take RETEVMO with food (with PPI) or modify its administration time (with H2 receptor antagonist or locally-acting antacid). (2.4, 7.1)
- Strong and Moderate CYP3A Inhibitors: Avoid coadministration. If coadministration cannot be avoided, reduce the RETEVMO dose. (2.6, 7.1)
- Strong and Moderate CYP3A Inducers: Avoid coadministration. (7.1)
- CYP2C8 and CYP3A Substrates: Avoid coadministration. If coadministration cannot be avoided, modify the substrate dosage as recommended in its product labeling. (7.2)
- Certain P-gp and BCRP Substrates: Avoid coadministration. If coadministration cannot be avoided, modify the substrate dosage as recommended in its product labeling. (7.2)

8 USE IN SPECIFIC POPULATIONS

- Lactation: Advise not to breastfeed. (8.2)
- Pediatric Use: Monitor open growth plates in pediatric patients. Consider interrupting or discontinuing RETEVMO if abnormalities occur. (8.4)

FULL PRESCRIBING INFORMATION

1 INDICATIONS AND USAGE

1.1 RET Fusion-Positive Non-Small Cell Lung Cancer

RETEVMO® is indicated for the treatment of adult patients with locally advanced or metastatic non-small cell lung cancer (NSCLC) with a rearranged during transfection (RET) gene fusion, as detected by an FDA-approved test.

1.2 RET-Mutant Medullary Thyroid Cancer

RETEVMO is indicated for the treatment of adult and pediatric patients 2 years of age and older with advanced or metastatic medullary thyroid cancer (MTC) with a RET mutation, as detected by an FDA-approved test, who require systemic therapy.

1.3 RET Fusion-Positive Thyroid Cancer

RETEVMO is indicated for the treatment of adult and pediatric patients 2 years of age and older with advanced or metastatic thyroid cancer with a RET gene fusion, as detected by an FDA-approved test, who require systemic therapy and who are radioactive iodine-refractory (if radioactive iodine is appropriate).

1.4 Other RET Fusion-Positive Solid Tumors

RETEVMO is indicated for the treatment of adult and pediatric patients 2 years of age and older with locally advanced or metastatic solid tumors with a RET gene fusion, as detected by an FDA-approved test, that have progressed on or following prior systemic treatment or who have no satisfactory alternative treatment options.

This indication is approved under accelerated approval based on overall response rate and duration of response [see Clinical Studies (14.4)]. Continued approval for this indication may be contingent upon verification and description of clinical benefit in confirmatory trial(s).

2 DOSAGE AND ADMINISTRATION

2.1 Patient Selection

Select patients for treatment with RETEVMO based on the presence of a RET gene fusion (NSCLC, thyroid cancer, or other solid tumors) or specific RET gene mutation (MTC) in tumor specimens [see Clinical Studies (14)]. Information on FDA-approved test(s) for the detection of RET gene fusions and RET gene mutations is available at: http://www.fda.gov/CompanionDiagnostics. An FDA-approved companion diagnostic test for the detection of RET gene fusions and RET gene mutations in plasma is not available.

2.2 Important Administration Instructions

- RETEVMO may be taken with or without food unless coadministered with a proton pump inhibitor (PPI) [see Dosage and Administration (2.4), Clinical Pharmacology (12.3)].
- Swallow the capsule or tablet whole. Do not crush or chew the capsules or tablets.
- For patients unable to swallow capsules or tablets or who are using a feeding tube, prepare and administer RETEVMO as a dispersion; only RETEVMO 40 mg tablets may be used to create the dispersion [see Dosage and Administration (2.8)]

2.3 Recommended Dosage

The recommended dosage of RETEVMO administered as recommended [see Dosage and Administration (2.2)] given until disease progression or unacceptable toxicity is shown in Table 1:

Table 1: Recommended RETEVMO Dosage
Population | RETEVMO Dosage
Adult and adolescent patients 12 years of age or older based on body weight
- Less than 50 kg | 120 mg twice daily
- 50 kg or greater | 160 mg twice daily
Pediatric patients 2 to less than 12 years of age based on body surface area
- 0.33 to 0.65 m^2 | 40 mg three times daily
- 0.66 to 1.08 m^2 | 80 mg twice daily
- 1.09 to 1.52 m^2 | 120 mg twice daily
- ≥1.53 m^2 | 160 mg twice daily
Dosing pediatric patients with body surface area less than 0.33 m^2 is not recommended

Missed Dose

Do not take a missed dose unless it is more than 6 hours until next scheduled dose.

Vomiting

If vomiting occurs after RETEVMO administration, do not take an additional dose and continue to the next scheduled time for the next dose.

2.4 Dosage Modifications for Concomitant Use of Acid-Reducing Agents

Avoid concomitant use of a PPI, a histamine-2 (H2) receptor antagonist, or a locally-acting antacid with RETEVMO [see Drug Interactions (7.1)]. If concomitant use cannot be avoided:

- Take RETEVMO with food when coadministered with a PPI.
- Take RETEVMO 2 hours before or 10 hours after administration of an H2 receptor antagonist.
- Take RETEVMO 2 hours before or 2 hours after administration of a locally-acting antacid.

2.5 Dosage Modifications for Adverse Reactions

The recommended dose reductions for adverse reactions are provided in Table 2.

Table 2: Recommended RETEVMO Dose Reductions for Adverse Reactions
Current RETEVMO Dosage | Dose Reduction
Current RETEVMO Dosage | First | Second | Third
40 mg three times daily | 40 mg twice daily | 40 mg once daily | permanently discontinue
80 mg twice daily | 40 mg twice daily | 40 mg once daily | permanently discontinue
120 mg twice daily | 80 mg twice daily | 40 mg twice daily | 40 mg once daily
160 mg twice daily | 120 mg twice daily | 80 mg twice daily | 40 mg twice daily
Permanently discontinue RETEVMO in patients unable to tolerate three dose reductions.

The recommended dosage modifications for adverse reactions are provided in Table 3.

Table 3: Recommended RETEVMO Dosage Modifications for Adverse Reactions
Adverse Reaction | Severity | Dosage Modification
Hepatotoxicity [see Warnings and Precautions (5.1)] | Grade 3 or Grade 4 | - Withhold RETEVMO and monitor AST/ALT once weekly until resolution to Grade 1 or baseline. - Resume at reduced dose by 2 dose levels and monitor AST and ALT once weekly until 4 weeks after reaching dose taken prior to the onset of Grade 3 or 4 increased AST or ALT. - Increase dose by 1 dose level after a minimum of 2 weeks without recurrence and then increase to dose taken prior to the onset of Grade 3 or 4 increased AST or ALT after a minimum of 4 weeks without recurrence.
Interstitial Lung Disease/ Pneumonitis [see Warnings and Precautions (5.2)] | Grade 2 | - Withhold RETEVMO until resolution. - Resume at a reduced dose. - Discontinue RETEVMO for recurrent ILD/pneumonitis.
Interstitial Lung Disease/ Pneumonitis [see Warnings and Precautions (5.2)] | Grade 3 or Grade 4 | - Discontinue RETEVMO for confirmed ILD/pneumonitis.
Hypertension [see Warnings and Precautions (5.3)] | Grade 3 | - Withhold RETEVMO for Grade 3 hypertension that persists despite optimal antihypertensive therapy. Resume at a reduced dose when hypertension is controlled.
Hypertension [see Warnings and Precautions (5.3)] | Grade 4 | - Discontinue RETEVMO.
QT Interval Prolongation [see Warnings and Precautions (5.4)] | Grade 3 | - Withhold RETEVMO until recovery to baseline or Grade 0 or 1. - Resume at a reduced dose or permanently discontinue RETEVMO.
QT Interval Prolongation [see Warnings and Precautions (5.4)] | Grade 4 | - Discontinue RETEVMO.
Hemorrhagic Events [see Warnings and Precautions (5.5)] | Grade 3 or Grade 4 | - Withhold RETEVMO until recovery to baseline or Grade 0 or 1. - Discontinue RETEVMO for severe or life-threatening hemorrhagic events.
Hypersensitivity Reactions [see Warnings and Precautions (5.6)] | Grades 1-3 | - Withhold RETEVMO until resolution of the event. Initiate corticosteroids. - Resume at a reduced dose by 3 dose levels while continuing corticosteroids. - Increase dose by 1 dose level each week until the dose taken prior to the onset of hypersensitivity is reached, then taper corticosteroids. - Discontinue RETEVMO for any severe skin reaction including Stevens Johnson Syndrome.
 | Recurrent Grade 3 or Grade 4 | - Discontinue RETEVMO.
Hypothyroidism [see Warnings and Precautions (5.9)] | Grade 3 or Grade 4 | - Withhold RETEVMO until resolution to Grade 1 or baseline. - Discontinue RETEVMO based on severity.
Other Adverse Reactions [see Adverse Reactions (6.1)] | Grade 3 or Grade 4 | - Withhold RETEVMO until recovery to baseline or Grade 0 or 1. - Resume at a reduced dose.

2.6 Dosage Modifications for Concomitant Use of Strong and Moderate CYP3A Inhibitors

Avoid concomitant use of strong and moderate CYP3A inhibitors with RETEVMO. If concomitant use of a strong or moderate CYP3A inhibitor cannot be avoided, reduce the RETEVMO dose as recommended in Table 4. After the inhibitor has been discontinued for 3 to 5 elimination half-lives, resume RETEVMO at the dose taken prior to initiating the CYP3A inhibitor [see Drug Interactions (7.1)].

Table 4: Recommended RETEVMO Dosage for Concomitant Use of Strong and Moderate CYP3A Inhibitors
Current RETEVMO Dosage | Recommended RETEVMO Dosage
 | Moderate CYP3A Inhibitor | Strong CYP3A Inhibitor
40 mg orally three times daily | 40 mg orally once daily | 40 mg orally once daily
80 mg orally twice daily | 40 mg orally twice daily | 40 mg orally twice daily
120 mg orally twice daily | 80 mg orally twice daily | 40 mg orally twice daily
160 mg orally twice daily | 120 mg orally twice daily | 80 mg orally twice daily

2.7 Dosage Modification for Severe Hepatic Impairment

Reduce the recommended dosage of RETEVMO for patients with severe hepatic impairment as recommended in Table 5 [see Use in Specific Populations (8.7)].

Table 5: Recommended RETEVMO Dosage for Severe Hepatic Impairment
Current RETEVMO Dosage | Recommended RETEVMO Dosage
40 mg orally three times daily | 40 mg orally twice daily
80 mg orally twice daily | 40 mg orally twice daily
120 mg orally twice daily | 80 mg orally twice daily
160 mg orally twice daily | 80 mg orally twice daily

2.8 Alternative Administration for Patients Unable to Swallow Tablets or Capsules

For patients unable to swallow whole capsules or tablets, the 40 mg tablet may be dispersed and administered orally or via gastrostomy or nasogastric tube. Use only the 40 mg tablet to make the dispersion.

RETEVMO 40 mg tablets for Oral Administration

To prepare RETEVMO tablet as a dispersion:

1. In a glass or medicine cup, add the correct number of 40 mg RETEVMO tablets required for the prescribed dose (1, 2, 3, or 4 tablets), to approximately 1 tablespoon (15 mL) of room temperature or chilled water or 100% carrot puree.
2. Stir intermittently until tablet(s) have dispersed (approximately 7 to 10 minutes). Some settling may occur and the dispersion may appear cloudy if water is used.
3. Administer the entire dispersion immediately.
4. Add 1 tablespoon (15 mL) of water to the glass or medicine cup, swirl or stir to collect any remaining medicine and administer immediately.
5. Discard RETEVMO dispersion if not taken within 2 hours.

RETEVMO 40 mg tablets for Feeding Tubes (Gastrostomy or Nasogastric Tube) Administration

Use only polyurethane (French size 8 or larger) or vinyl chloride (French size 10 or larger) nasogastric tube or silicone (French size 14 or larger) gastrostomy tube.

1. In a glass or medicine cup, add the correct number of 40 mg RETEVMO tablet(s) required for the prescribed dose (1, 2, 3, or 4 tablets), to a minimum of 10 mL of room temperature water.
2. Stir intermittently until tablet(s) have dispersed (approximately 7 to 10 minutes). Some settling may occur and the dispersion may appear cloudy.
3. Flush the feeding tube according to manufacturer's instructions.
4. Draw the dispersion into an enteral syringe and administer the dispersion via the feeding tube immediately.
5. Add 5 mL of water to the glass or medicine cup, swirl or stir to collect any remaining medicine, and deliver this rinse via the feeding tube using the same syringe.
6. Repeat rinse as necessary to ensure full dose is delivered.
7. Flush the feeding tube according to manufacturer's instructions.
8. Discard RETEVMO dispersion if not taken within 2 hours.

3 DOSAGE FORMS AND STRENGTHS

Capsules:

- 40 mg: gray opaque capsule imprinted with “Lilly”, “3977” and “40 mg” in black ink.
- 80 mg: blue opaque capsule imprinted with “Lilly”, “2980” and “80 mg” in black ink.

Tablets:

- 40 mg: light gray, film coated, round tablet debossed with “Ret 40” on one side and “5340” on the other side.
- 80 mg: dark red-purple, film coated, round tablet debossed with “Ret 80” on one side and “6082” on the other side.
- 120 mg: light purple, film coated, round tablet debossed with “Ret 120” on one side and “6120” on the other side.
- 160 mg: light pink, film coated, round tablet debossed with “Ret 160” on one side and “5562” on the other side.

4 CONTRAINDICATIONS

None.

5 WARNINGS AND PRECAUTIONS

5.1 Hepatotoxicity

Serious hepatic adverse reactions occurred in 3% of patients treated with RETEVMO. Increased AST occurred in 59% of patients, including Grade 3 or 4 events in 11% and increased ALT occurred in 55% of patients, including Grade 3 or 4 events in 12% [see Adverse Reactions (6.1)]. The median time to first onset for increased AST was 6 weeks (range: 1 day to 3.4 years) and increased ALT was 5.8 weeks (range: 1 day to 2.5 years).

Monitor ALT and AST prior to initiating RETEVMO, every 2 weeks during the first 3 months, then monthly thereafter and as clinically indicated. Withhold, reduce the dose or permanently discontinue RETEVMO based on the severity [see Dosage and Administration (2.5)].

5.2 Interstitial Lung Disease/Pneumonitis

Severe, life-threatening, and fatal interstitial lung disease (ILD)/pneumonitis can occur in patients treated with RETEVMO. ILD/pneumonitis occurred in 1.8% of patients who received RETEVMO, including 0.3% with Grade 3 or 4 events, and 0.3% with fatal reactions.

Monitor for pulmonary symptoms indicative of ILD/pneumonitis. Withhold RETEVMO and promptly investigate for ILD in any patient who presents with acute or worsening of respiratory symptoms which may be indicative of ILD (e.g., dyspnea, cough, and fever). Withhold, reduce the dose or permanently discontinue RETEVMO based on severity of confirmed ILD [see Dosage and Administration (2.5)].

5.3 Hypertension

Hypertension occurred in 41% of patients, including Grade 3 hypertension in 20% and Grade 4 in one (0.1%) patient [see Adverse Reactions (6.1)]. Overall, 6.3% had their dose interrupted and 1.3% had their dose reduced for hypertension. Treatment-emergent hypertension was most commonly managed with anti-hypertension medications.

Do not initiate RETEVMO in patients with uncontrolled hypertension. Optimize blood pressure prior to initiating RETEVMO. Monitor blood pressure after 1 week, at least monthly thereafter and as clinically indicated. Initiate or adjust anti-hypertensive therapy as appropriate. Withhold, reduce the dose, or permanently discontinue RETEVMO based on the severity [see Dosage and Administration (2.5)].

5.4 QT Interval Prolongation

RETEVMO can cause concentration-dependent QT interval prolongation [see Clinical Pharmacology (12.2)]. An increase in QTcF interval to >500 ms was measured in 7% of patients and an increase in the QTcF interval of at least 60 ms over baseline was measured in 20% of patients [see Adverse Reactions (6.1)]. RETEVMO has not been studied in patients with clinically significant active cardiovascular disease or recent myocardial infarction.

Monitor patients who are at significant risk of developing QTc prolongation, including patients with known long QT syndromes, clinically significant bradyarrhythmias, and severe or uncontrolled heart failure. Assess QT interval, electrolytes and TSH at baseline and periodically during treatment, adjusting frequency based upon risk factors including diarrhea. Correct hypokalemia, hypomagnesemia, and hypocalcemia prior to initiating RETEVMO and during treatment.

Monitor the QT interval more frequently when RETEVMO is concomitantly administered with strong and moderate CYP3A inhibitors or drugs known to prolong QTc interval. Withhold and reduce the dose or permanently discontinue RETEVMO based on the severity [see Dosage and Administration (2.5)].

5.5 Hemorrhagic Events

Serious including fatal hemorrhagic events can occur with RETEVMO. Grade ≥3 hemorrhagic events occurred in 3.1% of patients treated with RETEVMO, including 4 (0.5%) patients with fatal hemorrhagic events, including cerebral hemorrhage (n = 2), tracheostomy site hemorrhage (n = 1), and hemoptysis (n=1).

Permanently discontinue RETEVMO in patients with severe or life-threatening hemorrhage [see Dosage and Administration (2.5)].

5.6 Hypersensitivity

RETEVMO can cause hypersensitivity, including severe skin reactions such as Stevens Johnson Syndrome. All grade hypersensitivity occurred in 6% of patients receiving RETEVMO, including Grade 3 in 1.9%. The median time to onset was 1.9 weeks (range: 5 days to 2 years). Signs and symptoms of hypersensitivity included fever, rash and arthralgias or myalgias with concurrent decreased platelets or transaminitis. Stevens Johnsons Syndrome has been observed in the post-marketing setting [see Adverse Reactions (6.2)]. Discontinue RETEVMO in patients with Stevens Johnson Syndrome.

If hypersensitivity occurs, withhold RETEVMO and begin corticosteroids at a dose of 1 mg/kg prednisone (or equivalent). Upon resolution of the event, resume RETEVMO at a reduced dose and increase the dose of RETEVMO by 1 dose level each week as tolerated until reaching the dose taken prior to onset of hypersensitivity [see Dosage and Administration (2.5)]. Continue steroids until patient reaches target dose and then taper. Permanently discontinue RETEVMO for recurrent hypersensitivity.

5.7 Tumor Lysis Syndrome

Tumor lysis syndrome (TLS) occurred in 0.6% of patients with medullary thyroid carcinoma receiving RETEVMO [see Adverse Reactions (6.1)]. Patients may be at risk of TLS if they have rapidly growing tumors, a high tumor burden, renal dysfunction, or dehydration. Closely monitor patients at risk, consider appropriate prophylaxis including hydration, and treat as clinically indicated.

5.8 Risk of Impaired Wound Healing

Impaired wound healing can occur in patients who receive drugs that inhibit the vascular endothelial growth factor (VEGF) signaling pathway. Therefore, RETEVMO has the potential to adversely affect wound healing.

Withhold RETEVMO for at least 7 days prior to elective surgery. Do not administer for at least 2 weeks following major surgery and until adequate wound healing. The safety of resumption of RETEVMO after resolution of wound healing complications has not been established.

5.9 Hypothyroidism

RETEVMO can cause hypothyroidism. Hypothyroidism occurred in 13% of patients treated with RETEVMO; all reactions were Grade 1 or 2. Hypothyroidism occurred in 13% of patients (50/373) with thyroid cancer and 13% of patients (53/423) with other solid tumors including NSCLC [see Adverse Reactions (6.1)].

Monitor thyroid function before treatment with RETEVMO and periodically during treatment. Treat with thyroid hormone replacement as clinically indicated. Withhold RETEVMO until clinically stable or permanently discontinue RETEVMO based on severity [see Dosage and Administration (2.5)].

5.10 Embryo-Fetal Toxicity

Based on data from animal reproduction studies and its mechanism of action, RETEVMO can cause fetal harm when administered to a pregnant woman. Administration of selpercatinib to pregnant rats during organogenesis at maternal exposures that were approximately equal to those observed at the recommended human dose of 160 mg twice daily resulted in embryolethality and malformations.

Advise pregnant women and females of reproductive potential of the potential risk to a fetus. Advise females of reproductive potential to use effective contraception during treatment with RETEVMO and for 1 week after the last dose. Advise males with female partners of reproductive potential to use effective contraception during treatment with RETEVMO and for 1 week after the last dose [see Use in Specific Populations (8.1, 8.3)].

5.11 Slipped Capital Femoral Epiphysis/Slipped Upper Femoral Epiphysis in Pediatric Patients

Slipped capital femoral epiphysis/slipped upper femoral epiphysis (SCFE/SUFE) occurred in 1 adolescent (2.8% of 36 patients) receiving RETEVMO in LIBRETTO-121 and 1 adolescent (0.5% of 193 patients) receiving RETEVMO in LIBRETTO-531 [see Adverse Reactions (6.1)]. Monitor patients for symptoms indicative of SCFE/SUFE and treat as medically and surgically appropriate [see Adverse Reactions (6.1)].

6 ADVERSE REACTIONS

The following clinically significant adverse reactions are described elsewhere in the labeling:

- Hepatotoxicity [see Warnings and Precautions (5.1)]
- Interstitial Lung Disease / Pneumonitis [see Warnings and Precautions (5.2)]
- Hypertension [see Warnings and Precautions (5.3)]
- QT Interval Prolongation [see Warnings and Precautions (5.4)]
- Hemorrhagic Events [see Warnings and Precautions (5.5)]
- Hypersensitivity [see Warnings and Precautions (5.6)]
- Tumor Lysis Syndrome [see Warnings and Precautions (5.7)]
- Risk of Impaired Wound Healing [see Warnings and Precautions (5.8)]
- Hypothyroidism [see Warnings and Precautions (5.9)]
- Slipped Capital Femoral Epiphysis/Slipped Upper Femoral Epiphysis in Adolescent Patients [see Warnings and Precautions (5.11)]

6.1 Clinical Trials Experience

Because clinical trials are conducted under widely varying conditions, adverse reaction rates observed in the clinical trials of a drug cannot be directly compared to rates in the clinical trials of another drug and may not reflect the rates observed in practice.

The safety population described in the WARNINGS and PRECAUTIONS and below reflects exposure to RETEVMO as a single agent administered at 160 mg orally twice daily evaluated in 796 patients with advanced solid tumors in LIBRETTO-001 [see Clinical Studies (14)].

RET Gene Fusion or Gene Mutation Positive Solid Tumors

LIBRETTO-001

Among the 796 patients who received RETEVMO, 84% were exposed for 6 months or longer and 73% were exposed for greater than one year. Among these patients, 96% received at least one dose of RETEVMO at the recommended dosage of 160 mg orally twice daily.

The median age was 59 years (range: 15 to 92 years); 0.3% were pediatric patients 12 to 16 years of age; 51% were male; and 69% were White, 23% were Asian, and 3% were Black or African American; and 5% were Hispanic/Latino. The most common tumors were NSCLC (45%), MTC (40%), and non-medullary thyroid carcinoma (7%).

Serious adverse reactions occurred in 44% of patients who received RETEVMO. The most frequent serious adverse reactions (≥2% of patients) were pneumonia, pleural effusion, abdominal pain, hemorrhage, hypersensitivity, dyspnea, and hyponatremia. Fatal adverse reactions occurred in 3% of patients; fatal adverse reactions included sepsis (n = 6), respiratory failure (n = 5), hemorrhage (n = 4), pneumonia (n = 3), pneumonitis (n = 2), cardiac arrest (n=2), sudden death (n = 1), and cardiac failure (n = 1).

Permanent discontinuation due to an adverse reaction occurred in 8% of patients who received RETEVMO. Adverse reactions resulting in permanent discontinuation in ≥0.5% of patients included increased ALT (0.6%), fatigue (0.6%), sepsis (0.5%), and increased AST (0.5%).

Dosage interruptions due to an adverse reaction occurred in 64% of patients who received RETEVMO. Adverse reactions requiring dosage interruption in ≥5% of patients included increased ALT, increased AST, diarrhea, and hypertension.

Dose reductions due to an adverse reaction occurred in 41% of patients who received RETEVMO. Adverse reactions requiring dosage reductions in ≥2% of patients included increased ALT, increased AST, QT prolongation, fatigue, diarrhea, drug hypersensitivity, and edema.

The most common adverse reactions (≥25%) were edema, diarrhea, fatigue, dry mouth, hypertension, abdominal pain, constipation, rash, nausea, and headache.

The most common Grade 3 or 4 laboratory abnormalities (≥5%) were decreased lymphocytes, increased alanine aminotransferase (ALT), increased aspartate aminotransferase (AST), decreased sodium, and decreased calcium.

Table 6 summarizes the adverse reactions in LIBRETTO-001.

Table 6: Adverse Reactions (≥20%) in Patients Who Received RETEVMO in LIBRETTO-001
Adverse Reaction | RETEVMO (n = 796)
 | Grades 1-4# (%) | Grades 3-4 (%)
General Disorders and Administration Site Conditions
Edema^1 | 49 | 0.8*
Fatigue^2 | 46 | 3.1*
Arthralgia | 21 | 0.3*
Gastrointestinal Disorders
Diarrhea^3 | 47 | 5*
Dry Mouth | 43 | 0
Abdominal pain^4 | 34 | 2.5*
Constipation | 33 | 0.8*
Nausea | 31 | 1.1*
Vomiting | 22 | 1.8*
Vascular Disorders
Hypertension | 41 | 20
Skin and Subcutaneous Tissue Disorders
Rash^5 | 33 | 0.6*
Nervous System Disorders
Headache^6 | 28 | 1.4*
Respiratory, Thoracic and Mediastinal Disorders
Cough^7 | 24 | 0
Dyspnea^8 | 22 | 3.1
Blood and Lymphatic System Disorders
Hemorrhage^9 | 22 | 2.6
Investigations
Prolonged QT interval | 21 | 4.8*
^1 Edema includes edema peripheral, face edema, periorbital edema, eye edema, eyelid edema, orbital edema, localized edema, lymphedema, scrotal edema, peripheral swelling, scrotal swelling, swelling, swelling face, eye swelling, generalized edema, genital edema.
^2 Fatigue includes asthenia and malaise.
^3 Diarrhea includes defecation urgency, frequent bowel movements, gastrointestinal hypermotility, anal incontinence.
^4 Abdominal pain includes abdominal pain upper, abdominal pain lower, abdominal discomfort, abdominal tenderness, epigastric discomfort, gastrointestinal pain.
^5 Rash includes rash erythematous, rash macular, rash maculopapular, rash morbilliform, rash papular, rash pruritic, butterfly rash, exfoliative rash, rash follicular, rash generalized, rash vesicular.
^6 Headache includes sinus headache, tension headache.
^7 Cough includes productive cough, upper airway cough syndrome.
^8 Dyspnea includes dyspnea exertional, dyspnea at rest.
^9 Hemorrhage includes, epistaxis, hematuria, hemoptysis, contusion, rectal hemorrhage, vaginal hemorrhage, ecchymosis, hematochezia, petechiae, traumatic hematoma, anal hemorrhage, blood blister, blood urine present, cerebral hemorrhage, gastric hemorrhage, hemorrhage intracranial, hemorrhage subcutaneous, spontaneous hematoma, abdominal wall hematoma, angina bullosa hemorrhagica, conjunctival hemorrhage, disseminated intravascular coagulation, diverticulum intestinal hemorrhagic, eye hemorrhage, gastrointestinal hemorrhage, gingival bleeding, hematemesis, hemorrhagic stroke, hemorrhoidal hemorrhage, hepatic hemorrhage, hepatic hematoma, intraabdominal hemorrhage, laryngeal hemorrhage, lower gastrointestinal hemorrhage, melena, mouth hemorrhage, occult blood positive, post procedural hemorrhage, postmenopausal hemorrhage, pelvic hematoma, periorbital hematoma, periorbital hemorrhage, pharyngeal hemorrhage, pulmonary contusion, purpura, retinal hemorrhage, retroperitoneal hematoma, scleral hemorrhage, skin hemorrhage, subarachnoid hemorrhage, subdural hemorrhage, upper gastrointestinal hemorrhage, uterine hemorrhage, vessel puncture site hematoma.
* Only includes a grade 3 adverse reaction.
# Graded according to National Cancer Institute Common Terminology Criteria for Adverse Events (NCI CTCAE) version 4.03

Clinically relevant adverse reactions in ≤15% of patients who received RETEVMO include hypothyroidism (13%); pneumonia (11%), hypersensitivity (6%); interstitial lung disease/pneumonitis, chylothorax, chylous ascites or tumor lysis syndrome (all < 2%).

Table 7 summarizes the laboratory abnormalities in LIBRETTO-001.

Table 7: Select Laboratory Abnormalities (≥20%) Worsening from Baseline in Patients Who Received RETEVMO in LIBRETTO-001
Laboratory Abnormality | RETEVMO^1
Laboratory Abnormality | Grades 1-4# (%) | Grades 3-4 (%)
Chemistry
Increased AST | 59 | 11
Decreased calcium | 59 | 5.7
Increased ALT | 56 | 12
Decreased albumin | 56 | 2.3
Increased glucose | 53 | 2.8
Increased creatinine | 47 | 2.4
Decreased sodium | 42 | 11
Increased alkaline phosphatase | 40 | 3.4
Increased total cholesterol | 35 | 1.7
Increased potassium | 34 | 2.7
Decreased glucose | 34 | 1.0
Decreased magnesium | 33 | 0.6
Increased bilirubin | 30 | 2.8
Hematology
Decreased lymphocytes | 52 | 20
Decreased platelets | 37 | 3.2
Decreased hemoglobin | 28 | 3.5
Decreased neutrophils | 25 | 3.2
^1 Denominator for each laboratory parameter is based on the number of patients with a baseline and post-treatment laboratory value available, which ranged from 765 to 791 patients.
# Graded according to National Cancer Institute Common Terminology Criteria for Adverse Events (NCI CTCAE) version 4.03

LIBRETTO-121

The safety population described below reflects exposure to RETEVMO as a single agent at 92 mg/m^2 orally twice daily evaluated in 36 patients with advanced solid tumors harboring an activating RET alteration in LIBRETTO-121 [see Clinical Studies (14)]. Among the 36 pediatric and adolescent patients who received RETEVMO, 86% were exposed for 6 months or longer and 72% were exposed for greater than one year.

The median age was 13 years (range: 2 to 20 years); 31% were pediatric patients 2 to 12 years of age; 53% were male; and 47% were White, 28% were Asian, and 8% were Black or African American; and 19% were Hispanic/Latino. The most common cancers were MTC (42%), and papillary thyroid cancer (42%).

Serious adverse reactions occurred in 42% of patients who received RETEVMO. Serious adverse reactions occurring in more than 1 patient were vomiting and fracture (2 patients each).

Dosage interruptions due to an adverse reaction occurred in 42% of patients who received RETEVMO. Adverse reactions requiring dosage interruption in ≥5% of patients included increased ALT, increased AST, ascites, increased bilirubin, decreased neutrophils, and pyrexia.

Dose reductions due to an adverse reaction occurred in 22% of patients who received RETEVMO. Adverse reactions requiring dosage reductions in ≥2% of patients included increased ALT, decreased neutrophils, increased weight, and increased bilirubin.

The most common adverse reactions (≥25%) were musculoskeletal pain, diarrhea, nausea, hemorrhage, pyrexia, abdominal pain, headache, vomiting, fatigue, cough, rash, coronavirus infection, upper respiratory tract infection, and edema.

The most common Grade 3 or 4 laboratory abnormalities (≥5%) were decreased lymphocytes, decreased calcium, decreased hemoglobin, decreased neutrophils, increased ALT, decreased magnesium, and decreased potassium.

Table 8 summarizes the adverse reactions in LIBRETTO-121.

Table 8: Adverse Reactions (≥15%) in Patients Who Received RETEVMO in LIBRETTO-121
Adverse Reactions | RETEVMO N= 36
Adverse Reactions | Grades 1-4# % | Grades 3-4 %
Musculoskeletal and Connective Tissue Disorders
Musculoskeletal pain^1 | 58 | 0
Gastrointestinal Disorders
Diarrhea^2 | 47 | 2.8*
Nausea | 42 | 2.8*
Abdominal pain^3 | 36 | 0
Vomiting | 31 | 8*
Constipation | 22 | 6*
Blood and Lymphatic System Disorders
Hemorrhage^4 | 39 | 0
General Disorders and Administration Site Conditions
Pyrexia | 39 | 0
Fatigue^5 | 31 | 0
Edema^6 | 25 | 0
Nervous System Disorders
Headache | 33 | 0
Respiratory, Thoracic and Mediastinal Disorders
Cough | 31 | 0
Oropharyngeal pain | 22 | 0
Skin and Subcutaneous Tissue Disorders
Rash^7 | 28 | 0
Infections and Infestations
Coronavirus infection | 28 | 0
Upper respiratory tract infection | 28 | 2.8*
Urinary tract infection^8 | 19 | 2.8*
Endocrine Disorders
Hypothyroidism^9 | 22 | 0
Investigations
Increased weight | 19 | 11*
^1 Musculoskeletal pain includes arthralgia, back pain, bone pain, musculoskeletal chest pain, non-cardiac chest pain, neck pain, pain in extremity
^2 Diarrhea includes anal incontinence
^3 Abdominal pain includes abdominal pain upper, abdominal discomfort
^4 Hemorrhage includes epistaxis, hematuria, anal hemorrhage, blood urine present, hemoptysis, menorrhagia, mouth hemorrhage
^5 Fatigue includes asthenia, malaise
^6 Edema includes face edema, edema peripheral, periorbital edema, localized edema, generalized edema, gastrointestinal edema, swelling
^7 Rash includes rash maculopapular, rash erythematous, urticaria
^8 Urinary tract infection includes cystitis
^9 Hypothyroidism includes blood thyroid stimulating hormone increased, thyroglobulin increased
* No Grade 4 events were reported.
# Graded according to National Cancer Institute Common Terminology Criteria for Adverse Events (NCI CTCAE) version 5.0.

Clinically relevant adverse reactions in <15% of patients who received RETEVMO include dizziness (14%), electrocardiogram QT prolonged (14%), hypersensitivity (11%), stomatitis (14%), proteinuria (11%), hypertension (8%), decreased appetite (8%), erectile dysfunction (6%), chylous ascites (2.8%), dry mouth (2.8%), epiphysiolysis (2.8%), and pneumonia (2.8%).

Table 9 summarizes the laboratory abnormalities in LIBRETTO-121.

Table 9: Select Laboratory Abnormalities (≥15%) Worsening from Baseline in Patients Who Received RETEVMO in LIBRETTO-121
Laboratory Abnormality | RETEVMO1
Laboratory Abnormality | Grades 1-4# (%) | Grades 3-4 (%)
Chemistry
Decreased calcium | 61 | 11
Increased ALT | 58 | 8*
Decreased albumin | 53 | 0
Increased alkaline phosphatase | 50 | 0
Increased AST | 50 | 2.8*
Increased bilirubin | 31 | 2.8*
Increased cholesterol | 28 | 0
Decreased magnesium | 28 | 6
Increased potassium | 28 | 2.8
Increased creatinine | 19 | 2.8
Decreased potassium | 19 | 6
Decreased sodium | 17 | 0
Hematology
Decreased neutrophils | 40 | 8
Decreased hemoglobin | 36 | 11*
Increased hemoglobin | 33 | 2.8*
Decreased platelets | 28 | 2.8*
Decreased lymphocytes | 28 | 14
^1 Denominator for each laboratory parameter is based on the number of patients with a baseline and post-treatment laboratory value available, which ranged from 18 to 36 patients.
* No Grade 4 abnormalities were reported.
# Graded according to National Cancer Institute Common Terminology Criteria for Adverse Events (NCI CTCAE) version 5.

Treatment-naïve RET Fusion-Positive Non-Small Cell Lung Cancer

LIBRETTO-431

The safety population described below reflects exposure to RETEVMO as a single agent administered at 160 mg orally twice daily evaluated in 158 patients with unresectable locally advanced or metastatic RET fusion-positive NSCLC in LIBRETTO-431 [see Clinical Studies (14)]. Among the 158 patients who received RETEVMO, the median duration of exposure was 16.7 months (range: 5 days to 37.9 months); 87% were exposed for 6 months or longer and 70% were exposed for one year or longer.

The median age was 61 years (range: 31 to 87 years); 46% were male; and 36% were White, 58% were Asian, 1.3% were Black or African American, 1.3% were American Indian or Alaska Native, and 3.2% were missing.

Serious adverse reactions occurred in 35% of patients who received RETEVMO. The most frequent serious adverse reactions (≥2% of patients) were pleural effusion, and abnormal hepatic function. Fatal adverse reactions occurred in 4.4% of patients who received RETEVMO; fatal adverse reactions included myocardial infarction (n = 2), respiratory failure (n = 2), cardiac arrest, malnutrition, and sudden death (n = 1, each).

Permanent discontinuation due to an adverse reaction occurred in 10% of patients who received RETEVMO. Adverse reactions resulting in permanent discontinuation in ≥1% of patients included increased ALT (1.3%), and myocardial infarction (1.3%).

Dosage interruptions due to an adverse reaction occurred in 72% of patients who received RETEVMO. Adverse reactions requiring dosage interruption in ≥5% of patients included increased ALT, hypertension, increased AST, QT prolongation, diarrhea, and COVID-19 infection.

Dose reductions due to an adverse reaction occurred in 51% of patients who received RETEVMO. Adverse reactions requiring dose reductions in ≥5% of patients included increased ALT, increased AST, QT prolongation.

The most common adverse reactions (≥25%) in patients who received RETEVMO were hypertension, diarrhea, edema, dry mouth, rash, fatigue, abdominal pain, and musculoskeletal pain.

The most common Grade 3 or 4 laboratory abnormalities (≥5%) in patients who received RETEVMO were increased ALT, increased AST, and decreased lymphocytes.

Table 10 summarizes the adverse reactions in LIBRETTO-431.

Table 10: Adverse Reactions (≥15%) in Patients on Either Arm in LIBRETTO-431
Adverse Reaction | RETEVMO (n=158) |  | Chemotherapy with or without pembrolizumab (n=98)
Adverse Reaction | Grades 1-4# (%) | Grades 3-4 (%) | Grades 1-4# (%) | Grades 3-4 (%)
Vascular disorders
Hypertension | 48 | 20* | 7 | 3.1*
Gastrointestinal disorders
Diarrhea^1 | 44 | 1.3* | 24 | 2.0*
Dry mouth^2 | 39 | 0 | 6 | 0
Abdominal pain^3 | 25 | 0.6* | 19 | 2.0*
Constipation | 22 | 0 | 40 | 1.0*
Stomatitis^4 | 18 | 0 | 16 | 0
Nausea | 13 | 0 | 44 | 1.0*
Vomiting^5 | 13 | 0 | 23 | 1.0*
General disorders and administration site conditions
Edema^6 | 41 | 2.5* | 28 | 0
Fatigue^7 | 32 | 3.2* | 50 | 5*
Pyrexia | 13 | 0.6* | 23 | 0
Skin and subcutaneous tissue disorders
Rash^8 | 33 | 1.9* | 30 | 1.0*
Musculoskeletal and Connective Tissue Disorders
Musculoskeletal pain^9 | 25 | 0 | 28 | 0
Investigations
Electrocardiogram QT prolonged | 20 | 9* | 1.0 | 0
Infections and infestations
COVID-19 infection | 19 | 0.6* | 18 | 0
Metabolism and nutrition disorders
Decreased appetite | 17 | 0 | 34 | 2.0*
^1 Diarrhea includes diarrhea, anal incontinence.
^2 Dry mouth includes dry mouth, mucosal dryness.
^3 Abdominal pain includes abdominal pain, abdominal pain upper, abdominal discomfort, abdominal pain lower, gastrointestinal pain.
^4 Stomatitis includes stomatitis, mouth ulceration, mucosal inflammation.
^5 Vomiting includes vomiting, retching, regurgitation.
^6 Edema includes edema, edema peripheral, face edema, periorbital edema, swelling face, peripheral swelling, localized edema, eyelid edema, orbital edema, eye edema, scrotal edema, penile edema, orbital swelling, periorbital swelling.
^7 Fatigue includes fatigue, asthenia, malaise.
^8 Rash includes rash, rash maculopapular, skin exfoliation, rash erythematous, rash macular, dermatitis, urticaria, rash papular, dermatitis allergic, rash pustular, rash vesicular, genital rash.
^9 Musculoskeletal pain includes musculoskeletal pain, arthralgia, back pain, bone pain, musculoskeletal chest pain, non-cardiac chest pain, neck pain, pain in extremity.
* No Grade 4 abnormalities were reported.
# Graded according to National Cancer Institute Common Terminology Criteria for Adverse Events (NCI CTCAE) version 5.0.

Clinically relevant adverse reactions in <15% of patients who received RETEVMO include headache (14%); hemorrhage (13%); urinary tract infections (12%); hypothyroidism (9%); pneumonia (9%); dizziness (8%); interstitial lung disease/pneumonitis (4.4%); hypersensitivity, chylous ascites, and chylothorax (all < 2%).

Table 11 summarizes the laboratory abnormalities in LIBRETTO-431.

Table 11: Select Laboratory Abnormalities (≥20%) Worsening from Baseline in Patients on Either Arm in LIBRETTO-431
Laboratory Abnormality^1 | RETEVMO |  | Chemotherapy with or without pembrolizumab
Laboratory Abnormality^1 | Grades 1-4# (%) | Grades 3-4 (%) | Grades 1-4# (%) | Grades 3-4 (%)
Chemistry
ALT increased | 81 | 21 | 63 | 4.1
AST increased | 77 | 10 | 46 | 0
Alkaline phosphatase Increased | 35 | 1.3 | 22 | 0
Total bilirubin Increased | 52 | 1.3 | 9 | 0
Blood creatinine Increased | 23 | 0 | 21 | 0
Magnesium decreased | 16 | 0.6 | 8 | 0
Albumin decreased | 25 | 0 | 5 | 0
Calcium decreased | 53 | 1.9 | 24 | 1.0
Sodium decreased | 31 | 3.2 | 41 | 2.1
Potassium decreased | 17 | 1.3 | 15 | 1.0
Hematology
Platelets decreased | 53 | 3.2 | 39 | 5
Lymphocyte count decreased | 53 | 8 | 64 | 15
Hemoglobin decreased | 21 | 0 | 91 | 5
Neutrophil count decreased | 53 | 2.0 | 58 | 11
^1 Denominator for each laboratory parameter is based on the number of patients with a baseline and post-treatment laboratory value available: RETEVMO (range: 154 to 157 patients) and chemotherapy with or without pembrolizumab (range: 96 to 97 patients).
# Graded according to National Cancer Institute Common Terminology Criteria for Adverse Events (NCI CTCAE) version 5.0.

Increased Creatinine

In healthy subjects administered RETEVMO 160 mg orally twice daily, serum creatinine increased 18% after 10 days. Consider alternative markers of renal function if persistent elevations in serum creatinine are observed [see Clinical Pharmacology (12.3)].

RET-Mutant Medullary Thyroid Cancer

LIBRETTO-531

The safety population described below reflects exposure to RETEVMO as a single agent administered at 160 mg (adults) or at 92 mg/m^2 (adolescent, not to exceed 160 mg) orally twice daily, in patients with progressive, advanced, kinase inhibitor naïve, RET-mutant medullary thyroid cancer in LIBRETTO-531 [see Clinical Studies (14.2)]. Among the 193 patients who received RETEVMO, the observed median duration of exposure was 14.5 months (range: 25 days to 36 months); 80% were exposed for 6 months or longer and 59% were exposed for one year or longer.

The median age was 55 years (range: 12 to 84 years); 63% were male; and 69% were White, 28% were Asian, 2.9% were Black or African American and ethnicity was not routinely collected.

Serious adverse reactions occurred in 22% of patients who received RETEVMO. The most frequent serious adverse reactions were pneumonia and pyrexia (n = 3, each) and hypertension and urinary tract infection (n = 2, each). Fatal adverse reactions occurred in 2.1% of patients; fatal adverse reactions included COVID-19, diabetic ketoacidosis, multiple organ dysfunction syndrome, and sudden death (n=1 each).

Permanent discontinuation due to an adverse reaction occurred in 4.7% of patients who received RETEVMO. Adverse reactions resulting in permanent discontinuation were edema, multiple organ dysfunction syndrome, sudden death, AST increased, diabetic ketoacidosis, chronic kidney disease, retinopathy, COVID-19, and somatic symptom disorder (n = 1, each).

Dosage interruptions due to an adverse reaction occurred in 49% of patients who received RETEVMO. Adverse reactions requiring dosage omission in ≥5% of patients included ALT increased (9%) and hypertension (7%).

Dose reductions due to an adverse reaction occurred in 39% of patients who received RETEVMO. One adverse reaction, increased ALT (7%), required a dose reduction in ≥5% of patients.

The most common adverse reactions (≥25%) in patients who received RETEVMO were hypertension, edema, dry mouth, fatigue, and diarrhea.

The most common Grade 3 or 4 laboratory abnormalities (≥5%) in patients who received RETEVMO were decreased lymphocytes, increased ALT, decreased neutrophils, increased ALP, increased blood creatinine, decreased calcium, and increased AST.

Table 12 summarizes the adverse reactions in LIBRETTO-531.

Table 12: Adverse Reactions (≥10%) in Patients Who Received RETEVMO in LIBRETTO-531
Adverse Reaction | RETEVMO N = 193 |  | Cabozantinib or Vandetanib N = 97
Adverse Reaction | Grades 1-4# (%) | Grades 3-4 (%) | Grades 1-4# (%) | Grades 3-4 (%)
Vascular disorders
Hypertension^1 | 43 | 19* | 41 | 18*
General disorders and administration-site conditions
Edema^2 | 33 | 0 | 5 | 0
Fatigue^3 | 28 | 4.1* | 47 | 9*
Pyrexia | 12 | 1.0* | 2.1 | 0
Gastrointestinal disorders
Dry mouth^4 | 32 | 0.5* | 10 | 1.0*
Diarrhea^5 | 26 | 3.1* | 61 | 8*
Abdominal pain^6 | 18 | 0.5* | 21 | 2.1*
Constipation | 16 | 0 | 12 | 0
Stomatitis^7 | 14 | 0.5* | 42 | 13*
Pyrexia | 12 | 1.0* | 2.1 | 0
Nausea | 10 | 1.0* | 32 | 5*
Nervous system disorders
Headache^8 | 23 | 0.5* | 21 | 0
Skin and subcutaneous tissue disorders
Rash^9 | 19 | 1.6* | 27 | 4.1*
Reproductive system and breast disorders
Erectile dysfunction | 16 | 0 | 0 | 0
Investigations
Electrocardiogram QT prolonged^10 | 14 | 4.7* | 13 | 2.1*
Metabolism and nutrition disorders
Decreased appetite | 12 | 0.5* | 28 | 5*
Endocrine disorders
Hypothyroidism^11 | 11 | 0 | 21 | 0
^1 Hypertension includes hypertension, blood pressure increased.
^2 Edema includes edema peripheral, face edema, periorbital edema, swelling face, peripheral swelling, localized edema, eyelid edema, generalized edema, eye swelling, lymphoedema, orbital edema, eye edema, edema, edema genital, swelling, scrotal edema, scrotal swelling, angioedema, skin edema, testicular swelling, vulvovaginal swelling.
^3 Fatigue includes fatigue, asthenia, malaise.
^4 Dry mouth includes dry mouth, mucosal dryness.
^5 Diarrhea includes diarrhea, anal incontinence, defecation urgency, frequent bowel movements, gastrointestinal hypermotility.
^6 Abdominal pain included abdominal pain, abdominal pain upper, abdominal discomfort, abdominal pain lower, gastrointestinal pain.
^7 Stomatitis includes stomatitis, mouth ulceration, mucosal inflammation.
^8 Headache includes headache, sinus headache, tension headache.
^9 Rash includes rash, rash maculopapular, skin exfoliation, rash erythematous, rash macular, dermatitis, urticaria, rash pruritic, exfoliative rash, rash papular, dermatitis allergic, rash follicular, rash generalized, rash pustular, butterfly rash, rash morbilliform, rash vesicular.
^10 Electrocardiogram QT prolongation includes electrocardiogram QT prolonged, electrocardiogram QT interval abnormal.
^11 Hypothyroidism includes hypothyroidism, blood thyroid stimulating hormone increased.
* Only includes a Grade 3 adverse reaction
# Graded according to National Cancer Institute Common Terminology Criteria for Adverse Events (NCI-CTCAE) Version 5.0.

Clinically relevant adverse reactions in ≤10% of patients who received RETEVMO include dizziness (8%); urinary tract infections (8%); vomiting (8%); pneumonia, interstitial lung disease/pneumonitis, chylous ascites, and hypersensitivity (all < 2%).

Table 13 summarizes the laboratory abnormalities in LIBRETTO-531.

Table 13: Select Laboratory Abnormalities (≥5%) Worsening from Baseline in Patients Who Received RETEVMO in LIBRETTO-531
Laboratory Abnormality | RETEVMO^1 |  | Cabozantinib or Vandetanib^1
Laboratory Abnormality | Grades 1-4# % | Grades 3-4 % | Grades 1-4# % | Grades 3-4 %
Chemistry
Calcium decreased | 55 | 5 | 62 | 11
ALT increased | 53 | 16 | 72 | 7*
AST increased | 47 | 5 | 68 | 3.2*
Alkaline phosphatase increased | 37 | 6 | 28 | 5
Total bilirubin increased | 32 | 1.1 | 30 | 3.2*
Blood creatinine increased | 27 | 6 | 16 | 8
Sodium decreased | 20 | 3.2* | 16 | 0
Albumin decreased | 11 | 1.1 | 7 | 0
Magnesium decreased | 9 | 3.3 | 26 | 9
Potassium decreased | 8 | 0 | 22 | 4.4*
Hematology
Lymphocyte count decreased | 41 | 18 | 36 | 13
Neutrophil count decreased | 33 | 14 | 42 | 19
Platelets decreased | 28 | 1.1 | 34 | 1.1*
Hemoglobin decreased | 18 | 2.1* | 23 | 2.1*
^1 Denominator for each laboratory parameter is based on the number of patients with a baseline and post-treatment laboratory value available: RETEVMO (range: 183 to 191 patients) and chemotherapy with or without cabozantinib or vandetanib (range: 91 to 94 patients).
* Only includes a Grade 3 laboratory abnormality
# Graded according to National Cancer Institute Common Terminology Criteria for Adverse Events (NCI CTCAE) version 5.0

Increased Creatinine

In healthy subjects administered RETEVMO 160 mg orally twice daily, serum creatinine increased 18% after 10 days. Consider alternative markers of renal function if persistent elevations in serum creatinine are observed [see Clinical Pharmacology (12.3)].

6.2 Postmarketing Experience

The following adverse reaction has been identified during post-approval use of RETEVMO. Because such reactions are reported voluntarily from a population of uncertain size, it is not always possible to reliably estimate their frequency or establish a causal relationship to drug exposure.

Skin and subcutaneous tissue disorders: Stevens-Johnson Syndrome

7 DRUG INTERACTIONS

7.1 Effects of Other Drugs on RETEVMO

Acid-Reducing Agents

Concomitant use of RETEVMO with acid-reducing agents decreases selpercatinib plasma concentrations [see Clinical Pharmacology (12.3)], which may reduce RETEVMO anti-tumor activity.

Avoid concomitant use of PPIs, H2 receptor antagonists, and locally-acting antacids with RETEVMO. If coadministration cannot be avoided, take RETEVMO with food (with a PPI) or modify its administration time (with a H2 receptor antagonist or a locally-acting antacid) [see Dosage and Administration (2.4)].

Strong and Moderate CYP3A Inhibitors

Concomitant use of RETEVMO with a strong or moderate CYP3A inhibitor increases selpercatinib plasma concentrations [see Clinical Pharmacology (12.3)], which may increase the risk of RETEVMO adverse reactions, including QTc interval prolongation.

Avoid concomitant use of strong and moderate CYP3A inhibitors with RETEVMO. If concomitant use of strong and moderate CYP3A inhibitors cannot be avoided, reduce the RETEVMO dosage and monitor the QT interval with ECGs more frequently [see Dosage and Administration (2.6), Warning and Precautions (5.4)].

Strong and Moderate CYP3A Inducers

Concomitant use of RETEVMO with a strong or moderate CYP3A inducer decreases selpercatinib plasma concentrations [see Clinical Pharmacology (12.3)], which may reduce RETEVMO anti-tumor activity.

Avoid coadministration of strong or moderate CYP3A inducers with RETEVMO.

7.2 Effects of RETEVMO on Other Drugs

CYP2C8 and CYP3A Substrates

RETEVMO is a moderate CYP2C8 inhibitor and a weak CYP3A inhibitor. Concomitant use of RETEVMO with CYP2C8 and CYP3A substrates increases their plasma concentrations [see Clinical Pharmacology (12.3)], which may increase the risk of adverse reactions related to these substrates. Avoid coadministration of RETEVMO with CYP2C8 and CYP3A substrates where minimal concentration changes may lead to increased adverse reactions. If coadministration cannot be avoided, follow recommendations for CYP2C8 and CYP3A substrates provided in their approved product labeling.

Certain P-gp and BCRP Substrates

RETEVMO is a P-gp and BCRP inhibitor. Concomitant use of RETEVMO with P-gp or BCRP substrates increases their plasma concentrations [see Clinical Pharmacology (12.3)], which may increase the risk of adverse reactions related to these substrates. Avoid coadministration of RETEVMO with P-gp or BCRP substrates where minimal concentration changes may lead to increased adverse reactions. If coadministration cannot be avoided, follow recommendations for P-gp and BCRP substrates provided in their approved product labeling.

7.3 Drugs that Prolong QT Interval

RETEVMO is associated with QTc interval prolongation [see Warnings and Precautions (5.4), Clinical Pharmacology (12.2)]. Monitor the QT interval with ECGs more frequently in patients who require treatment with concomitant medications known to prolong the QT interval.

8 USE IN SPECIFIC POPULATIONS

8.1 Pregnancy

Risk Summary

Based on findings from animal studies, and its mechanism of action [see Clinical Pharmacology (12.1)], RETEVMO can cause fetal harm when administered to a pregnant woman. There are no available data on RETEVMO use in pregnant women to inform drug-associated risk. Administration of selpercatinib to pregnant rats during the period of organogenesis resulted in embryolethality and malformations at maternal exposures that were approximately equal to the human exposure at the clinical dose of 160 mg twice daily. Advise pregnant women of the potential risk to a fetus.

In the U.S. general population, the estimated background risk of major birth defects and miscarriage in clinically recognized pregnancies is 2% to 4% and 15% to 20%, respectively.

Data

Animal Data

Selpercatinib administration to pregnant rats during the period of organogenesis at oral doses ≥100 mg/kg [approximately 3.6 times the human exposure based on the area under the curve (AUC) at the clinical dose of 160 mg twice daily] resulted in 100% post-implantation loss. At the dose of 50 mg/kg [approximately equal to the human exposure (AUC) at the clinical dose of 160 mg twice daily], 6 of 8 females had 100% early resorptions; the remaining 2 females had high levels of early resorptions with only 3 viable fetuses across the 2 litters. All viable fetuses had decreased fetal body weight and malformations (2 with short tail and one with small snout and localized edema of the neck and thorax).

8.2 Lactation

Risk Summary

There are no data on the presence of selpercatinib or its metabolites in human milk or on their effects on the breastfed child or on milk production. Because of the potential for serious adverse reactions in breastfed children, advise women not to breastfeed during treatment with RETEVMO and for 1 week after the last dose.

8.3 Females and Males of Reproductive Potential

Based on animal data, RETEVMO can cause embryolethality and malformations at doses resulting in exposures less than or equal to the human exposure at the clinical dose of 160 mg twice daily [see Use in Specific Populations (8.1)].

Pregnancy Testing

Verify pregnancy status in females of reproductive potential prior to initiating RETEVMO [see Use in Specific Populations (8.1)].

Contraception

Females

Advise female patients of reproductive potential to use effective contraception during treatment with RETEVMO and for 1 week after the last dose.

Males

Advise males with female partners of reproductive potential to use effective contraception during treatment with RETEVMO and for 1 week after the last dose.

Infertility

RETEVMO may impair fertility in females and males of reproductive potential [see Use in Specific Populations (8.4), Nonclinical Toxicology (13.1)].

8.4 Pediatric Use

The safety and effectiveness of RETEVMO have been established in pediatric patients aged 2 years and older for the treatment of:

- advanced or metastatic medullary thyroid cancer (MTC) with a RET mutation who require systemic therapy
- advanced or metastatic thyroid cancer with a RET gene fusion who require systemic therapy and are radioactive iodine-refractory (if radioactive iodine is appropriate)
- locally advanced or metastatic solid tumors with a RET gene fusion that have progressed on or following prior systemic treatment or who have no satisfactory alternative treatment options.

Use of RETEVMO for these indications is supported by evidence from adequate and well-controlled studies in adult and pediatric patients with additional pharmacokinetic and safety data in pediatric patients aged 2 years and older [see Adverse Reactions (6.1), Clinical Pharmacology (12.3), Clinical Studies (14.2, 14.3, 14.4)]. The predicted exposures of selpercatinib in pediatric patients at the recommended dosages were within the range of values observed in patients ≥ 12 years and ≥ 50 kg in body weight receiving the approved recommended dosage of 160 mg twice daily [see Clinical Pharmacology (12.3)].

The safety and effectiveness of RETEVMO have not been established in these indications in patients aged less than 2 years.

The safety and effectiveness of RETEVMO have not been established in pediatric patients for other indications [see Indications and Usage (1)].

Juvenile Animal Toxicity Data

In a juvenile rat toxicity study, animals were dosed daily with selpercatinib from post-natal day 21 to day 70 (approximately equivalent to a human child to late adolescent). Selpercatinib increased physeal thickness of multiple bones, extending into the metaphysis and associated with decreased trabecular bone, which was not reversible at doses approximately equivalent to or greater than the adult human exposure at the clinical dose of 160 mg twice daily. Growth plate changes were associated with impairment of bone modeling, resulting in decreased femur length and with reduction in bone mineral density. Selpercatinib also induced reversible hypocellularity of bone marrow in males at ≥30 mg/kg (approximately equivalent to or greater than the adult human exposure at the clinical dose of 160 mg twice daily), and reversible alterations of dentin composition at ≥50 mg/kg (approximately 3 times the adult human exposure at the clinical dose of 160 mg twice daily). Irreversible, dose-dependent degeneration of testicular germinal epithelium, with vacuolation of Sertoli cells and corresponding depletion of spermatozoa in the epididymides, was also observed at ≥ 30 mg/kg (approximately equivalent to or greater than the adult human exposure at the clinical dose of 160 mg twice daily) and affected male reproductive performance at 50 mg/kg (approximately 3 times the adult human exposure at the clinical dose of 160 mg twice daily). Females exhibited delay in attainment of vaginal patency, a marker of sexual maturity, at 125 mg/kg (approximately 4 times the adult human exposure at the clinical dose of 160 mg twice daily); this effect was associated with lower mean body weight. Similar effects in irregular thickening of growth plates in adult rats and minipigs, and tooth dysplasia and malocclusion, resulting in tooth loss in adult rats were observed in repeat dose studies of up to 13-week duration with selpercatinib.

Monitor growth plates in pediatric patients with open growth plates. Consider interrupting or discontinuing therapy based on the severity of any growth plate abnormalities and based on an individual risk-benefit assessment.

8.5 Geriatric Use

Of 796 patients who received RETEVMO, 34% (268 patients) were ≥65 years of age and 9% (74 patients) were ≥75 years of age. No overall differences were observed in the safety or effectiveness of RETEVMO between patients who were ≥65 years of age and younger patients.

8.6 Renal Impairment

No dosage modification is recommended for patients with mild to severe renal impairment [estimated Glomerular Filtration Rate (eGFR) ≥15 to 89 mL/min, estimated by Modification of Diet in Renal Disease (MDRD) equation]. The recommended dosage has not been established for patients with end-stage renal disease (ESRD) [see Clinical Pharmacology (12.3)].

8.7 Hepatic Impairment

Reduce the dose when administering RETEVMO to patients with severe [total bilirubin > 3 to 10 × upper limit of normal (ULN) and any AST] hepatic impairment [see Dosage and Administration (2.7)].

No dosage modification is recommended for patients with mild (total bilirubin ≤ ULN with AST > ULN or total bilirubin > 1 to 1.5 × ULN with any AST) or moderate (total bilirubin > 1.5 to 3 × ULN and any AST) hepatic impairment.

Monitor for RETEVMO-related adverse reactions in patients with hepatic impairment [see Clinical Pharmacology (12.3)].

11 DESCRIPTION

RETEVMO contains selpercatinib, a kinase inhibitor. The molecular formula for selpercatinib is C29H31N7O3 and the molecular weight is 525.61 g/mol. The chemical name is 6-(2-hydroxy-2-methylpropoxy)-4-(6-(6-((6-methoxypyridin-3-yl)methyl)-3,6-diazabicyclo[3.1.1]heptan-3-yl)pyridin-3-yl)pyrazolo[1,5-a]pyridine-3-carbonitrile. Selpercatinib has the following chemical structure:

Selpercatinib is a white to light yellow powder that is slightly hygroscopic. The aqueous solubility of selpercatinib is pH dependent, from sparingly soluble at low pH to practically insoluble at neutral pH.

RETEVMO capsules contain either 40 mg or 80 mg of selpercatinib in hard gelatin capsules for oral use. Each capsule contains inactive ingredients of colloidal silicon dioxide and microcrystalline cellulose. The 40 mg capsule shell is composed of gelatin, titanium dioxide, ferric oxide black and black ink. The 80 mg capsule shell is composed of gelatin, titanium dioxide, FD&C blue #1 and black ink. The black ink is composed of shellac, potassium hydroxide and ferric oxide black.

RETEVMO tablets contain 40 mg, 80 mg, 120 mg, or 160 mg of selpercatinib as film coated, debossed tablets for oral use. Each tablet contains inactive ingredients of croscarmellose sodium, hydroxypropyl cellulose, mannitol, microcrystalline cellulose, and sodium stearyl fumarate. The tablet film coating material contains polyvinyl alcohol, titanium dioxide, polyethylene glycol, and talc. Additionally, the film coating of the 40 mg, 80 mg, and 120 mg tablets contains ferrosoferric oxide and the film coating of the 80 mg, 120 mg, and 160 mg tablets contain ferric oxide.

12 CLINICAL PHARMACOLOGY

12.1 Mechanism of Action

Selpercatinib is a kinase inhibitor. Selpercatinib inhibited wild-type RET and multiple mutated RET isoforms as well as VEGFR1 and VEGFR3 with IC50 values ranging from 0.92 nM to 67.8 nM. In other enzyme assays, selpercatinib also inhibited FGFR 1, 2, and 3 at higher concentrations that were still clinically achievable. In cellular assays, selpercatinib inhibited RET at approximately 60-fold lower concentrations than FGFR1 and 2 and approximately 8-fold lower concentration than VEGFR3.

Certain point mutations in RET or chromosomal rearrangements involving in-frame fusions of RET with various partners can result in constitutively activated chimeric RET fusion proteins that can act as oncogenic drivers by promoting cell proliferation of tumor cell lines. In in vitro and in vivo tumor models, selpercatinib demonstrated anti-tumor activity in cells harboring constitutive activation of RET proteins resulting from gene fusions and mutations, including CCDC6-RET, KIF5B-RET, RET V804M, and RET M918T. In addition, selpercatinib showed anti-tumor activity in mice intracranially implanted with a patient-derived RET fusion positive tumor.

12.2 Pharmacodynamics

Exposure-Response Relationship

Selpercatinib exposure-response relationships and the time course of pharmacodynamic response have not been fully characterized.

Cardiac Electrophysiology

The effect of RETEVMO on the QTc interval was evaluated in a thorough QT study in healthy subjects. The largest mean increase in QTc is predicted to be 10.6 msec (upper 90% confidence interval: 12.1 msec) at the mean steady-state maximum concentration (Cmax) observed in patients after administration of 160 mg twice daily. The increase in QTc was concentration-dependent.

12.3 Pharmacokinetics

The pharmacokinetics of selpercatinib capsules were evaluated in patients with locally advanced or metastatic solid tumors administered 160 mg twice daily unless otherwise specified. The capsule and tablet dosage forms of selpercatinib are bioequivalent. Steady state selpercatinib AUC and Cmax increased in a slightly greater than dose proportional manner over the dose range of 20 mg once daily to 240 mg twice daily [0.06 to 1.5 times the maximum recommended total daily dosage].

Steady-state was reached by approximately 7 days and the median accumulation ratio after administration of 160 mg twice daily was 3.4-fold. Mean steady-state selpercatinib [coefficient of variation (CV%)] Cmax was 2,980 (53%) ng/mL and AUC0-24h was 51,600 (58%) ng*h/mL.

Absorption

The median tmax of selpercatinib is 2 hours. The mean absolute bioavailability of RETEVMO capsules is 73% (60% to 82%) in healthy subjects.

Effect of Food

For both the capsule and tablet dosage forms no clinically significant differences in selpercatinib AUC or Cmax were observed following administration of a high-fat meal (approximately 900 calories, 58 grams carbohydrate, 56 grams fat and 43 grams protein) in healthy subjects.

Distribution

The apparent volume of distribution (Vss/F) of selpercatinib is 203 L.

Protein binding of selpercatinib is 96% in vitro and is independent of concentration. The blood-to-plasma concentration ratio is 0.7.

Elimination

The apparent clearance (CL/F) of selpercatinib is 6 L/h in patients and the half-life is 32 hours following oral administration of RETEVMO in healthy subjects.

Metabolism

Selpercatinib is metabolized predominantly by CYP3A4. Following oral administration of a single radiolabeled 160 mg dose of selpercatinib to healthy subjects, unchanged selpercatinib constituted 86% of the radioactive drug components in plasma.

Excretion

Following oral administration of a single radiolabeled 160 mg dose of selpercatinib to healthy subjects, 69% of the administered dose was recovered in feces (14% unchanged) and 24% in urine (12% unchanged).

Specific Populations

The apparent volume of distribution and clearance of selpercatinib increase with increasing body weight (9.6 kg to 179 kg).

No clinically significant differences in the pharmacokinetics of selpercatinib were observed based on age (2 years to 92 years), sex, or mild, moderate, or severe renal impairment (eGFR ≥15 to 89 mL/min). The effect of ESRD on selpercatinib pharmacokinetics has not been studied.

Pediatric patients

The exposures of selpercatinib in pediatric patients are comparable to those in adult patients administered at the recommended dosages.

Patients with Hepatic Impairment

The selpercatinib AUC0-INF increased 1.1-fold in subjects with mild (total bilirubin ≤ ULN with AST > ULN or total bilirubin > 1 to 1.5 × ULN with any AST), 1.3-fold in subjects with moderate (total bilirubin > 1.5 to 3 × ULN and any AST), and 1.8-fold in subjects with severe (total bilirubin > 3 to 10 × ULN and any AST) hepatic impairment, compared to subjects with normal hepatic function.

Drug Interaction Studies

Clinical Studies and Model-Informed Approaches

Proton-Pump Inhibitors (PPI): Coadministration with multiple daily doses of omeprazole (PPI) decreased selpercatinib AUC0-INF and Cmax when RETEVMO was administered fasting. Coadministration with multiple daily doses of omeprazole did not significantly change the selpercatinib AUC0-INF and Cmax when RETEVMO was administered with food (Table 14).

Table 14: Change in Selpercatinib Exposure After Coadministration with PPI
 | Selpercatinib AUC 0-INF | Selpercatinib Cmax
RETEVMO fasting | Reference | Reference
RETEVMO fasting + PPI | ↓ 69% | ↓ 88%
RETEVMO with a high-fat meal^1 + PPI | ↑ 2% | ↓ 49%
RETEVMO with a low-fat meal^2 + PPI | No change | ↓ 22%
^1 High-fat meal: approximately 150, 250, and 500-600 calories from protein, carbohydrate, and fat, respectively; approximately 800 to 1,000 calories total.
^2 Low-fat meal: approximately 390 calories and 10 g of fat.

H2 Receptor Antagonists: No clinically significant differences in selpercatinib pharmacokinetics were observed when coadministered with multiple daily doses of ranitidine (H2 receptor antagonist) given 10 hours prior to and 2 hours after the RETEVMO dose (administered fasting).

Strong CYP3A Inhibitors: Coadministration of multiple doses of itraconazole (strong CYP3A inhibitor) increased the selpercatinib AUC0-INF 2.3-fold and Cmax 1.3-fold.

Moderate CYP3A Inhibitors: Coadministration of multiple doses of diltiazem, fluconazole, or verapamil (moderate CYP3A inhibitors) is predicted to increase the selpercatinib AUC 1.6 to 2-fold and Cmax 1.5 to 1.8-fold.

Strong CYP3A Inducers: Coadministration of multiple doses of rifampin (strong CYP3A inducer) decreased the selpercatinib AUC0-INF by 87% and Cmax by 70%.

Moderate CYP3A Inducers: Coadministration of multiple doses of bosentan or efavirenz (moderate CYP3A inducers) is predicted to decrease the selpercatinib AUC by 40-70% and Cmax by 34-57%.

Weak CYP3A Inducers: Coadministration of multiple doses of modafinil (weak CYP3A inducer) is predicted to decrease the selpercatinib AUC by 33% and Cmax by 26%.

CYP2C8 Substrates: Coadministration of RETEVMO with repaglinide (sensitive CYP2C8 substrate) increased the repaglinide AUC0-INF 2.9-fold and Cmax 1.9-fold.

CYP3A Substrates: Coadministration of RETEVMO with midazolam (sensitive CYP3A substrate) increased the midazolam AUC0-INF 1.5-fold and Cmax 1.4-fold.

P-glycoprotein (P-gp) Substrates: Coadministration of RETEVMO with dabigatran (P-gp substrate) increased the dabigatran AUC0-INF 1.4-fold and Cmax 1.4-fold.

BCRP Substrates: Coadministration of RETEVMO with rosuvastatin (BCRP substrate) increased the rosuvastatin AUC0-INF by 1.9-fold and Cmax by 1.7-fold.

P-gp Inhibitors: No clinically significant differences in selpercatinib pharmacokinetics were observed when coadministered with a single dose of rifampin (P-gp inhibitor).

MATE1 Substrates: No clinically significant differences in glucose levels were observed when metformin (MATE1 substrate) was coadministered with selpercatinib.

In Vitro Studies

CYP Enzymes: Selpercatinib does not inhibit or induce CYP1A2, CYP2B6, CYP2C9, CYP2C19, or CYP2D6 at clinically relevant concentrations.

Transporter Systems: Selpercatinib inhibits MATE1. Selpercatinib may increase serum creatinine by decreasing renal tubular secretion of creatinine via inhibition of MATE1 [see Adverse Reactions (6.1)].

Selpercatinib does not inhibit OAT1, OAT3, OCT1, OCT2, OATP1B1, OATP1B3, BSEP, and MATE2-K at clinically relevant concentrations.

Selpercatinib is a substrate for P-gp and BCRP, but not for OAT1, OAT3, OCT1, OCT2, OATP1B1, OATP1B3, MATE1, or MATE2-K.

13 NONCLINICAL TOXICOLOGY

13.1 Carcinogenesis, Mutagenesis, Impairment of Fertility

Selpercatinib was not carcinogenic in a 2-year study in rats when administered by daily oral gavage at doses up to 20 mg/kg in males or 40 mg/kg in females (approximately equal to the human exposure by AUC at the 160 mg twice daily clinical dose). Selpercatinib was not carcinogenic in a 6-month study in rasH2 transgenic mice when administered by daily oral gavage at doses of up to 60 mg/kg.

Selpercatinib was not mutagenic in the in vitro bacterial reverse mutation (Ames) assays, with or without metabolic activation, or clastogenic in the in vitro micronucleus assay in human peripheral lymphocytes, with or without metabolic activation. Selpercatinib was positive in the in vivo micronucleus assay in rats at concentrations >7 times the Cmax at the human dose of 160 mg twice daily.

In general toxicology studies, male rats and minipigs exhibited testicular degeneration which was associated with luminal cell debris and/or reduced luminal sperm in the epididymis at selpercatinib exposures approximately 0.4 (rat) and 0.1 (minipig) times the clinical exposure by AUC at the 160 mg twice daily clinical dose. In a dedicated fertility study in male rats, administration of selpercatinib at doses up to 30 mg/kg/day (approximately twice the clinical exposure by AUC at the 160 twice daily clinical dose) for 28 days prior to cohabitation with untreated females did not affect mating or have clear effects on fertility. Males did, however, display a dose-dependent increase in testicular germ cell depletion and spermatid retention at doses ≥3 mg/kg (~0.2 times the clinical exposure by AUC at the 160 twice daily clinical dose) accompanied by altered sperm morphology at 30 mg/kg.

In a dedicated fertility study in female rats treated with selpercatinib for 15 days before mating to Gestational Day 7, there were decreases in the number of estrous cycles at a dose of 75 mg/kg (approximately equal to the human exposure by AUC at the 160 mg twice daily clinical dose). While selpercatinib did not have clear effects on mating performance or ability to become pregnant at any dose level, half of females at the 75 mg/kg dose level had 100% nonviable embryos. At the same dose level in females with some viable embryos there were increases in post-implantation loss. In a 3-month general toxicology study in minipigs, there were findings of decreased or absent corpora lutea at a selpercatinib dose of 15 mg/kg (approximately 0.3 times to the human exposure by AUC at the 160 mg twice daily clinical dose). Corpora luteal cysts were present in the minipig at selpercatinib doses ≥2 mg/kg (approximately 0.07 times the human exposure by AUC at the 160 mg twice daily clinical dose).

14 CLINICAL STUDIES

14.1 RET Fusion-Positive Non-Small Cell Lung Cancer

LIBRETTO-001

The efficacy of RETEVMO was evaluated in patients with advanced RET fusion-positive NSCLC enrolled in a multicenter, open-label, multi-cohort clinical trial (LIBRETTO-001, NCT03157128). The study enrolled patients with advanced or metastatic RET fusion-positive NSCLC who had progressed on platinum-based chemotherapy and patients with locally advanced (stage III who were not candidates for surgical resection or definitive chemoradiation) or metastatic NSCLC without prior systemic therapy in separate cohorts. Identification of a RET gene alteration was prospectively determined in local laboratories using next generation sequencing (NGS), polymerase chain reaction (PCR), fluorescence in situ hybridization (FISH) or other local testing methods. Adult patients received RETEVMO 160 mg orally twice daily until unacceptable toxicity or disease progression; patients enrolled in the dose escalation phase were permitted to adjust their dose to 160 mg twice daily. The major efficacy outcome measures were confirmed overall response rate (ORR) and duration of response (DOR), as determined by a blinded independent review committee (BIRC) according to RECIST v1.1.

RET Fusion-Positive NSCLC Previously Treated with Platinum Chemotherapy

Efficacy was evaluated in 247 patients with RET fusion-positive NSCLC previously treated with platinum chemotherapy enrolled into a cohort of LIBRETTO-001.

The median age was 61 years (range: 23 to 81); 57% were female; 44% were White, 48% were Asian, 4.9% were Black or African American; and 2.8% were Hispanic/Latino. ECOG performance status was 0-1 (97%) or 2 (3%) and 97% of patients had metastatic disease. Patients received a median of 2 prior systemic therapies (range 1–15); 58% had prior anti-PD1/PD-L1 therapy. RET fusions were detected in 94% of patients using NGS (84.6% tumor samples; 9.3% blood or plasma samples), 4.0% using FISH, 1.6% using PCR and 0.4% by other local testing methods.

Efficacy results for previously treated RET fusion-positive NSCLC are summarized in Table 15.

Table 15: Efficacy Results in LIBRETTO-001 (RET Fusion-Positive NSCLC Previously Treated with Platinum Chemotherapy)
 | RETEVMO (n = 247)
Overall Response Rate^1 (95% CI) | 61% (55%, 67%)
Complete response | 7.3%
Partial response | 54%
Duration of Response
Median in months (95% CI) | 28.6 (20, NE)
% with ≥ 12 months^2 | 63%
^1 Confirmed overall response rate assessed by BIRC.
^2 Based on observed duration of response.
NE = not estimable

For the 144 patients who received an anti-PD-1 or anti-PD-L1 therapy, either sequentially or concurrently with platinum-based chemotherapy, an exploratory subgroup analysis of ORR was 63% (95% CI: 54%, 70%) and the median DOR was 28.6 months (95% CI: 14.8, NE).

Among the 247 patients with previously treated RET fusion-positive NSCLC, 16 had measurable CNS metastases at baseline as assessed by BIRC. One patient received radiation therapy (RT) to the brain within 2 months prior to study entry. Responses in intracranial lesions were observed in 14 of these 16 patients; 39% of responders had an intracranial DOR of ≥ 12 months.

Treatment-naïve RET Fusion-Positive NSCLC

Efficacy was evaluated in 69 patients with treatment-naïve RET fusion-positive NSCLC enrolled into a cohort of LIBRETTO-001.

The median age was 63 years (range 23 to 92); 62% were female; 70% were White, 19% were Asian, and 6% were Black or African American. ECOG performance status was 0-1 (94%) or 2 (6%) and 99% of patients had metastatic disease. RET fusions were detected in 91% of patients using NGS (60.9% tumor samples; 30.4% in blood), 7.2% using FISH and 1.4% using PCR.

Efficacy results for treatment naïve RET fusion-positive NSCLC are summarized in Table 16.

Table 16: Efficacy Results in LIBRETTO-001 (Treatment-Naïve RET Fusion-Positive NSCLC)
 | RETEVMO (n =69)
Overall Response Rate^1 (95% CI) | 84% (73%, 92%)
Complete response | 5.8%
Partial response | 78%
Duration of Response
Median in months (95% CI) | 20.2 (13, NE)
% with ≥ 12 months^2 | 50%
^1 Confirmed overall response rate assessed by BIRC.
^2 Based on observed duration of response.
NE = not estimable

Among the 69 patients with treatment-naïve RET fusion-positive NSCLC, 5 had measurable CNS metastases at baseline as assessed by BIRC. Two patients received RT to the brain within 2 months prior to study entry. Responses in intracranial lesions were observed in 4 of these 5 patients; 38% of responders had an intracranial DOR of ≥ 12 months.

LIBRETTO-431

The efficacy of RETEVMO was evaluated in patients with unresectable, locally advanced or metastatic, RET fusion-positive NSCLC enrolled in a multicenter, open-label, active-controlled, randomized trial (LIBRETTO-431, NCT04194944). The trial evaluated RETEVMO compared to platinum-based and pemetrexed chemotherapy with or without pembrolizumab in patients with RET fusion-positive, unresectable locally advanced or metastatic NSCLC with no previous systemic therapy for metastatic disease.

Patients (N=261) were randomized to receive either RETEVMO (160 mg orally twice daily) in continuous 21-day cycles or pemetrexed intravenously (IV) (500 mg per square meter of body-surface area) along with the investigator’s choice of platinum therapy (carboplatin IV [AUC 5, maximum dose 750 mg] or cisplatin IV [75 mg per square meter]) with or without pembrolizumab IV (200 mg) every 21 days. Treatment continued until disease progression or unacceptable toxicity. Crossover from the control arm to RETEVMO was permitted following disease progression. Patients were stratified according to geographic region (East Asia vs. elsewhere), brain metastases at baseline (presence vs. absence or unknown), and the investigator’s intent (before randomization) to treat the patient with or without pembrolizumab. Tumor assessments were performed every 6 weeks for two assessments, then every 9 weeks for four assessments, and then every 12 weeks thereafter.

The major efficacy outcome measure was progression-free survival (PFS) in patients intended to be treated with chemotherapy in combination with pembrolizumab and in the overall study population as determined by a blinded independent review committee (BIRC) according to RECIST v1.1. Other efficacy outcome measures included overall survival (OS) and overall response rate (ORR).

A total of 212 patients were enrolled in LIBRETTO-431 with an intent to treat with pembrolizumab if randomized to the control arm (129 into RETEVMO arm and 83 into chemotherapy with pembrolizumab arm). The median age was 61.5 years (range: 31 to 84 years); 47% were male; 41% White, 55% Asian, and 0.9% Black or African American, 1.4% American Indian or Alaska Native, 1.9% were race not reported; ethnicity was not reported in 96% of patients. ECOG performance status was 0-1 (97%) or 2 (3%), 68% were never smokers, 93% of patients had metastatic disease, and 14% had measurable intracranial metastases at baseline, as determined by a neuroradiologic BIRC. RET fusions were detected in 60% of patients using NGS and 40% using PCR (89% tumor samples; 11% in blood).

Efficacy results from the pre-planned interim efficacy analysis are summarized in Table 17.

Table 17: Efficacy Results in LIBRETTO-431: RETEVMO versus Chemotherapy with Pembrolizumab
 | RETEVMO (n = 129) | Chemotherapy with pembrolizumab (n = 83)
Progression-Free Survival
Number (%) of patients with an event | 49 (38%) | 49 (59%)
Medians in months (95% CI) | 24.8 (16.9, NE) | 11.2 (8.8, 16.8)
Hazard ratio^1 (95% CI) | 0.46 (0.31, 0.70)
p-value^2 | 0.0002
Overall Response Rate (95% CI) | 84% (76, 90) | 65% (54, 75)
Complete response | 7% | 6%
Partial response | 77% | 59%
Duration of Response
Median in months (95% CI) % with ≥ 12 months^3 | 24.2 (17.9, NE) 60% | 11.5 (9.7, 23.3) 30%
^1 Based on the stratified Cox proportional hazard model, stratified by geographic location (East Asia versus elsewhere), brain metastases at baseline according to investigator (presence versus absence or unknown).
^2 Based on stratified log-rank test, stratified by geographic location (East Asia versus elsewhere), brain metastases at baseline according to investigator (presence versus absence or unknown).
^3 Based on observed duration of response.
NE = not estimable

Figure 1: Kaplan-Meier Curves of Progression-Free Survival in LIBRETTO-431: RETEVMO versus Chemotherapy with Pembrolizumab

Among the 212 randomized patients, 29 had measurable CNS metastases at baseline as assessed by BIRC. Responses in intracranial lesions were observed in 14 of 17 patients treated with RETEVMO and 7 of 12 patients treated with chemotherapy with pembrolizumab.

Overall survival was immature at the time of the PFS interim analysis. At the time of an updated descriptive analysis of OS (43% of prespecified OS events needed for the final analysis), a total of 49 (31%) and 26 (25%) patients died in the RETEVMO and the control arm, respectively. The OS HR was 1.26 (95% CI: 0.78, 2.04). Overall survival may be affected by the imbalance in post-progression therapies. Of 68 control arm patients who had disease progression, 50 patients (74%) received RETEVMO at progression. Of 71 RETEVMO arm patients who had disease progression, 16 (23%) received chemotherapy and/or immune checkpoint inhibitor therapy, and 44 (62%) continued receiving RETEVMO.

14.2 RET-Mutant Medullary Thyroid Cancer

LIBRETTO-001

The efficacy of RETEVMO was evaluated in patients with RET-mutant MTC enrolled in a multicenter, open-label, multi-cohort clinical trial (NCT03157128). The study enrolled patients with advanced or metastatic RET-mutant MTC who had been previously treated with cabozantinib or vandetanib (or both) and patients with advanced or metastatic RET-mutant MTC who were naïve to cabozantinib and vandetanib in separate cohorts.

RET-Mutant MTC Previously Treated with Cabozantinib or Vandetanib

Efficacy was evaluated in 55 patients with RET-mutant advanced MTC who had previously treated with cabozantinib or vandetanib enrolled into a cohort of LIBRETTO-001.

The median age was 57 years (range: 17 to 84); 66% were male; 89% were White, 7% were Hispanic/Latino, and 1.8% were Black. ECOG performance status was 0-1 (95%) or 2 (5%) and 98% of patients had metastatic disease. Patients received a median of 2 prior systemic therapies (range 1 – 8). RET mutation status was detected in 82% of patients using NGS (78% tumor samples; 4% blood or plasma), 16% using PCR, and 2% using an unknown test. The protocol excluded patients with synonymous, frameshift or nonsense RET mutations; the specific mutations used to identify and enroll patients are described in Table 18.

Table 18: Mutations used to Identify and Enroll Patients with RET-Mutant MTC in LIBRETTO-001
RET Mutation Type^1 | Previously Treated (n = 55) | Cabozantinib/ Vandetanib Naïve (n = 88) | Total (n = 143)
M918T | 33 | 49 | 82
Extracellular cysteine mutation^2 | 7 | 20 | 27
V804M or V804L | 5^4 | 6 | 11
Other^3 | 10 | 13 | 23
^1 Somatic or germline mutations; protein change.
^2 Extracellular cysteine mutations involving cysteine residues 609, 611, 618, 620, 630, and 634.
^3 Other included: K666N (1), D631_L633delinsV (2), D631_L633delinsE (5), D378_G385delinsE (1), D898_E901del (2), A883F (4), E632_L633del (4), L790F (2), T636_V637insCRT(1), D898_E901del + D903_S904delinsEP (1).
^4 One patient also had a M918T mutation.

Efficacy results for RET-mutant MTC are summarized in Table 19.

Table 19: Efficacy Results in LIBRETTO-001 (RET-Mutant MTC Previously Treated with Cabozantinib or Vandetanib)
 | RETEVMO (n = 55)
Overall Response Rate^1 (95% CI) | 76% (63%, 87%)
Complete response | 18%
Partial response | 58%
Duration of Response
Median in months (95% CI) | 45.3 (29.9, NE)
% with ≥12 months^2 | 76%
^1 Confirmed overall response rate assessed by BIRC.
^2 Based on observed duration of response.
NE = not estimable

Cabozantinib and Vandetanib-naïve RET-Mutant MTC

Efficacy was evaluated in 88 patients with RET-mutant MTC who were cabozantinib and vandetanib treatment-naïve enrolled into a cohort of LIBRETTO-001.

The median age was 58 years (range: 15 to 82) with two patients (2.3%) aged 12 to 16 years; 66% were male; and 86% were White, 4.5% were Asian, and 2.3% were Hispanic/Latino. ECOG performance status was 0-1 (97%) or 2 (3.4%). All patients (100%) had metastatic disease and 18% had received 1 or 2 prior systemic therapies (including 8% kinase inhibitors, 4.5% chemotherapy, 2.3% anti-PD1/PD-L1 therapy, and 1.1% radioactive iodine). RET mutation status was detected in 77.3% of patients using NGS (75.0% tumor samples; 2.3% blood samples), 18.2% using PCR, and 4.5% using an unknown test. The mutations used to identify and enroll patients are described in Table 18.

Efficacy results for cabozantinib and vandetanib-naïve RET-mutant MTC are summarized in Table 20.

Table 20: Efficacy Results in LIBRETTO-001 (Cabozantinib and Vandetanib-naïve RET-Mutant MTC)
 | RETEVMO (n = 88)
Overall Response Rate^1 (95% CI) | 81% (71%, 88%)
Complete response | 28%
Partial response | 52%
Duration of Response
Median in months (95% CI) | NR (51.3, NE)
% with ≥12 months^2 | 90%
^1 Confirmed overall response rate assessed by BIRC.
^2 Based on observed duration of response.
NR = not reached, NE = not estimable

LIBRETTO-531

LIBRETTO-531 was a randomized (2:1), multicenter, open-label study (NCT04211337) in adults and adolescents with advance or metastatic RET-mutant MTC. The study evaluated the efficacy of RETEVMO versus physicians’ choice of cabozantinib or vandetanib in patients with progressive, advanced, kinase inhibitor naïve, RET-mutant medullary thyroid cancer.

Patients were randomized to receive either RETEVMO (160 mg twice daily) or physicians’ choice of cabozantinib (140 mg once daily) or vandetanib (300 mg once daily). Patients were stratified based on RET mutation (M918T vs. other) and intended treatment if randomized to the control arm (cabozantinib vs. vandetanib). The primary outcome was progression-free survival (PFS), as determined by a blinded independent review committee (BIRC) according to RECIST v1.1.

The median age was 55 years (range: 12 to 84), 63% were male, 58% were White, 23% were Asian, 2.4% were Black or African American, and 17% had unknown race. ECOG performance status was 0-1 (98%) or 2 (1.0%) with 0.7% unknown status. 77% of patients had metastatic disease and 6 patients (2.1%) had received 1 prior systemic therapy. RET mutation status was detected in 90% of patients using NGS (89% tumor samples; 8% blood or plasma), and 10% using PCR. Of patients enrolled in LIBRETTO-531, 63% had M918T RET mutations and 37% had other RET mutations.

Efficacy results for LIBRETTO-531 based on the preplanned interim efficacy analysis are provided in Table 21 and Figure 2. At the time of this analysis, overall survival data were immature with 18 deaths observed (14% of pre-specified events).

Table 21: Efficacy Results in LIBRETTO-531: RETEVMO versus Cabozantinib or Vandetanib
 | RETEVMO N = 193 | Cabozantinib or Vandetanib N = 98
PFS
Number (%) of patients with an event | 26 (14%) | 33 (34%)
Median in months (95% CI) | NR (NE, NE) | 16.8 (12.2, 25.1)
Hazard ratio (95% CI)1 | 0.280 (95% CI: 0.165, 0.475)
p-value^2 | <0.0001
Overall Response Rate
ORR (95% CI) | 69% (62%, 76%) | 39% (29%, 49%)
Complete response | 12% | 4%
Partial response | 58% | 35%
Duration of Response
Median in months (95% CI) | NR (NE, NE) | 16.6 (10.4, NE)
Median follow-up time (months) | 11.1 | 12.8
Data from the pre-planned interim efficacy analysis.
^1 Based on the stratified Cox proportional hazard model.
^2 Based on stratified log-rank test.
NR = Not reached; NE = not evaluable

Figure 2: Kaplan-Meier Curves of Progression-Free Survival in LIBRETTO-531: RETEVMO versus Cabozantinib or Vandetanib

Patient-reported overall side effect impact was evaluated weekly in 222 patients (RETEVMO N = 145; cabozantinib or vandetanib N=77) who received at least one dose of treatment by at least 6 months prior to the data cutoff date and responded to the Functional Assessment of Cancer Therapy item GP5 (FACT GP5). Patient-reported overall side effect impact was derived as a proportion of time on treatment with high side effect bother (defined as response of 3 “Quite a bit” or 4 “Very much”) per FACT GP5.

Patient-reported overall side effect impact results for LIBRETTO-531 are provided in Table 22.

Table 22. Descriptive Summary of Patient-reported Overall Side Effect Impact While on Treatment in LIBRETTO-531
 | RETEVMO (N=145) | Cabozantinib or Vandetanib (N=77)
Mean proportion of time with high side effect bother (95% CI) | 8% (4.8%, 10%) | 24% (17%, 31%)
% Patients with high side effect bother 0% of time ≤25% of time | 61% 90% | 30% 66%

Patient-reported overall side effect impact results were supported by a lower incidence of treatment discontinuation due to adverse reactions for RETEVMO (4.7%) compared to cabozantinib or vandetanib (27%) in patients who received at least one dose of study treatment. The median time on treatment at the data cutoff was 14.5 months in the RETEVMO arm and 8.3 months in the cabozantinib or vandetanib arm in patients who received at least one dose of study treatment.

LIBRETTO-121

The efficacy of RETEVMO was evaluated in pediatric and young adult patients with advanced RET-activated solid tumors enrolled in a multicenter, open-label, multi-cohort clinical trial (LIBRETTO-121, NCT03899792). Patients received RETEVMO 92 mg/m^2 orally twice daily until disease progression, unacceptable toxicity, or other reason for treatment discontinuation. Tumor assessments were performed every 8 weeks for one year, then every 12 weeks; responses were assessed according to RECIST 1.1 per BIRC.

Efficacy was evaluated in 14 patients with RET-mutant MTC who were non-responsive to available therapies or had no standard systemic curative therapy available. The median age was 14 years (range 2 to 20); 64% were male; 71% were White, 14% were Black or African American; and 14% were Hispanic/Latino. Patients had metastatic (71%) or locally advanced (29%) disease; 43% had measurable disease at baseline; 21% had received prior systemic therapy. RET-mutant status was detected in 79% of patients using NGS tumor samples and in 21% using PCR.

Efficacy results for RET-mutant MTC in pediatric and young adult patients are summarized in Table 23.

Table 23: Efficacy Results in LIBRETTO-121 (RET-Mutant MTC)
 | RETEVMO (n = 14)
Overall Response Rate^1 (95% CI) | 57% (29, 82)
Complete response | 36%
Partial response | 21%
Duration of Response
Median in months (range) | Not reached (8.3+, 49.7+)
% with ≥ 18 months^2 | 88%
% with ≥ 24 months^2 | 75%
^1 Confirmed overall response rate assessed by BIRC.
^2 Based on observed duration of response.
+ Denotes ongoing response.

14.3 RET Fusion-Positive Thyroid Cancer

LIBRETTO-001

The efficacy of RETEVMO was evaluated in patients with advanced RET fusion-positive thyroid cancer enrolled in a multicenter, open-label, multi-cohort clinical trial (LIBRETTO-001, NCT03157128). Efficacy was evaluated in 65 patients with RET fusion-positive thyroid cancer who were radioactive iodine (RAI)-refractory (if RAI was an appropriate treatment option) and were systemic therapy naïve and patients who were previously treated, in separate cohorts.

The median age was 59 years (range 20 to 88); 49% were male; 65% were White, 20% were Asian, 4.6% were Black or African American; and 11% were Hispanic/Latino. ECOG performance status was 0-1 (94%) or 2 (6%). All (100%) patients had metastatic disease with primary tumor histologies including papillary thyroid cancer (83%), poorly differentiated thyroid cancer (9%), anaplastic thyroid cancer (6%) and Hurthle cell thyroid cancer (1.5%). Previously treated patients had received a median of 1 prior therapy (range 1–4). RET fusion-positive status was detected in 97% of patients using NGS (89% tumor samples; 8% blood or plasma samples), and 3% using other local testing methods.

Efficacy results for RET fusion-positive thyroid cancer are summarized in Table 24.

Table 24: Efficacy Results in LIBRETTO-001 (RET Fusion-Positive Thyroid Cancer)
 | RETEVMO Previously Treated (n = 41) | RETEVMO Systemic Therapy Naïve (n = 24)
Overall Response Rate^1 (95% CI) | 85% (71%, 94%) | 96% (79%, 100%)
Complete response | 12% | 21%
Partial response | 73% | 75%
Duration of Response
Median in months (95% CI) | 26.7 (12.1, NE) | NE (42.8, NE)
% with ≥12 months^2 | 54 | 65
^1 Confirmed overall response rate assessed by BIRC.
^2 Based on observed duration of response.
NE = not estimable

Responses were observed in patients with each histology represented, including 3 of 4 patients with anaplastic thyroid cancer (all partial responses) and 6 of 6 patients with poorly differentiated thyroid cancer (1 complete response, 5 partial responses).

LIBRETTO-121

The efficacy of RETEVMO was evaluated in pediatric and young adult patients with advanced RET-activated solid tumors enrolled in a multicenter, open-label, multi-cohort clinical trial (LIBRETTO-121, NCT03899792) [see Clinical Studies (14.2)].

Efficacy was evaluated in 15 patients with RET fusion-positive thyroid cancer who were non-responsive to available therapies or had no standard systemic curative therapy available. The median age was 12 years (range 6 to 20); 53% were male; 40% were White, 47% were Asian, 13% were other races; and 27% were Hispanic/Latino. Patients had metastatic (87%) or locally advanced (13%) disease and 100% had papillary thyroid cancer histology; 47% had measurable disease at baseline; 20% had received prior systemic therapy. RET fusion-positive status was detected in 93% of patients using NGS tumor samples and in 7% using FISH. Efficacy results for RET fusion-positive thyroid cancer in pediatric and young adult patients are summarized in Table 25.

Table 25: Efficacy Results in LIBRETTO-121 (RET Fusion-Positive Thyroid Cancer)
 | RETEVMO (n = 15)
Overall Response Rate^1 (95% CI) | 53% (27, 79)
Complete response | 27%
Partial response | 27%
Duration of Response
Median in months (range) | Not reached (12.9+, 44.2)
% with ≥ 18 months^2 | 88%
% with ≥ 24 months^2 | 75%
^1 Confirmed overall response rate assessed by BIRC.
^2 Based on observed duration of response.
+ Denotes ongoing response.

14.4 Other RET Fusion-Positive Solid Tumors

LIBRETTO-001

The efficacy of RETEVMO was evaluated in patients with locally advanced or metastatic RET fusion-positive solid tumors enrolled in a multicenter, open-label, multi-cohort clinical trial (LIBRETTO-001, NCT03157128). Efficacy was evaluated in 41 patients with RET fusion-positive tumors other than NSCLC and thyroid cancer with disease progression on or following prior systemic treatment or who had no satisfactory alternative treatment options.

The median age was 50 years (range 21 to 85), 54% were female, 68% were White, 24% were Asian, and 4.9% were Black; and 7% were Hispanic/Latino. ECOG performance status was 0-1 (95%) or 2 (5%) and 95% of patients had metastatic disease. Thirty-seven patients (90%) received prior systemic therapy (median 2 [range 0 – 9]; 32% received 3 or more). The most common cancers were pancreatic adenocarcinoma (27%), colorectal (24%), salivary (10%) and unknown primary (7%). RET fusion-positive status was detected in 97.6% of patients using NGS and 2.4% using FISH.

Efficacy results for RET fusion-positive solid tumors other than NSCLC and thyroid cancer are summarized in Table 26 and Table 27.

Table 26: Efficacy Results in LIBRETTO-001 (Other RET Fusion-Positive Solid Tumors)
 | RETEVMO (n = 41)
Overall Response Rate^1 (95% CI) | 44% (28, 60)
Complete response | 4.9%
Partial response | 39%
Duration of Response
Median in months (95% CI) | 24.5 (9.2, NE)
% with ≥6 months^2 | 67%
^1 Confirmed overall response rate assessed by BIRC.
^2 Based on observed duration of response.
NE = not estimable

Table 27: Efficacy Results by Tumor Type in LIBRETTO-001 (Other RET Fusion-Positive Solid Tumors)
Tumor Type | Patients (n = 41) | ORR^1,2 |  | DOR Range (months)
 |  | n (%) | 95% CI
Pancreatic adenocarcinoma | 11 | 6 (55%) | (23, 83) | 2.5, 38.3+
Colorectal | 10 | 2 (20%) | (2.5, 56) | 5.6, 13.3
Salivary | 4 | 2 (50%) | (7, 93) | 5.7, 28.8+
Unknown primary | 3 | 1 (33%) | (0.8, 91) | 9.2
Breast | 2 | PR, CR | NA | 2.3+, 17.3
Sarcoma (soft tissue) | 2 | PR, SD | NA | 14.9+
Xanthogranuloma | 2 | NE, NE | NA | NA
Carcinoid (bronchial) | 1 | PR | NA | 24.1+
Carcinoma of the skin | 1 | NE | NA | NA
Cholangiocarcinoma | 1 | PR | NA | 5.6+
Ovarian | 1 | PR | NA | 14.5+
Pulmonary carcinosarcoma | 1 | NE | NA | NA
Rectal neuroendocrine | 1 | NE | NA | NA
Small intestine | 1 | CR | NA | 24.5
+ denotes ongoing response.
^1 Confirmed overall response rate assessed by BIRC.
^2 Best overall response for each patient is presented for tumor types with ≤2 patients.
CI = confidence interval, CR = complete response, DOR = duration of response, NA = not applicable, NE = not evaluable, ORR = overall response rate, PR = partial response, SD = stable disease.

LIBRETTO-121

The efficacy of RETEVMO was evaluated in pediatric and young adult patients with advanced RET-activated solid tumors enrolled in a multicenter, open-label, multi-cohort clinical trial (LIBRETTO-121, NCT03899792) [see Clinical Studies (14.2)].

Efficacy was evaluated in 3 patients with locally advanced refractory RET-fusion positive other solid tumors who were unresponsive to available therapies or had no standard systemic curative therapy available. The median age was 15 years (range 6 to 15). One patient with congenital infantile fibrosarcoma and one patient with a spindle cell sarcoma had a partial response. One patient with malignant peripheral nerve sheath tumor did not respond. Responses were observed in patients with RET fusion-positive thyroid cancer [see Clinical Studies (14.3)].

16 HOW SUPPLIED/STORAGE AND HANDLING

How Supplied

RETEVMO capsules are supplied as follows:

Capsule Strength | Description | Package Configuration | NDC Number
40 mg | Gray opaque, imprinted with “Lilly”, “3977” and “40 mg” in black ink | 60 count bottle | NDC 0002-3977-60
80 mg | Blue opaque, imprinted with “Lilly”, “2980” and “80 mg” in black ink | 60 count bottle | NDC 0002-2980-60
80 mg | Blue opaque, imprinted with “Lilly”, “2980” and “80 mg” in black ink | 120 count bottle | NDC 0002-2980-26

RETEVMO tablets are supplied in bottles with desiccant in the following configurations:

Tablet Strength | Description | Package Configuration | NDC Number
40 mg | Light gray, film coated, round tablets debossed with “Ret 40” on one side and “5340” on the other side | 60 count bottle | NDC 0002-5340-60
80 mg | Dark red-purple, film coated, round tablets debossed with “Ret 80” on one side and ”6082” on the other side | 60 count bottle | NDC 0002-6082-60
120 mg | Light purple, film coated, round tablets debossed with “Ret 120” on one side and “6120” on the other side | 60 count bottle | NDC 0002-6120-60
160 mg | Light pink, film coated, round tablets debossed with Ret “160” on one side and “5562” on the other side | 60 count bottle | NDC 0002-5562-60

Storage and Handling

Store at 20°C to 25°C (68°F to 77°F); excursions between 15°C and 30°C (59°F to 86°F) are permitted [see USP Controlled Room Temperature].

17 PATIENT COUNSELING INFORMATION

Advise the patient to read the FDA-approved patient labeling (Patient Information).

Hepatotoxicity

Advise patients that hepatotoxicity can occur and to immediately contact their healthcare provider for signs or symptoms of hepatotoxicity [see Warnings and Precautions (5.1)].

Interstitial Lung Disease (ILD)/Pneumonitis

Advise patients that ILD/ pneumonitis can occur and to contact their healthcare provider immediately for signs or symptoms of ILD including new or worsening cough or shortness of breath [see Warnings and Precautions (5.2)].

Hypertension

Advise patients that they will require regular blood pressure monitoring and to contact their healthcare provider if they experience symptoms of increased blood pressure or elevated readings [see Warnings and Precautions (5.3)].

QT Prolongation

Advise patients that RETEVMO can cause QTc interval prolongation and to inform their healthcare provider if they have any QTc interval prolongation symptoms, such as syncope [see Warnings and Precautions (5.4)].

Hemorrhagic Events

Advise patients that RETEVMO may increase the risk for bleeding and to contact their healthcare provider if they experience any signs or symptoms of bleeding [see Warnings and Precautions (5.5)].

Hypersensitivity Reactions

Advise patients to monitor for signs and symptoms of hypersensitivity reactions, particularly during the first month of treatment [see Warnings and Precautions (5.6)].

Tumor Lysis Syndrome

Advise patients to contact their healthcare provider promptly to report any signs and symptoms of TLS [see Warnings and Precautions (5.7)].

Risk of Impaired Wound Healing

Advise patients that RETEVMO may impair wound healing. Advise patients to inform their healthcare provider of any planned surgical procedure [see Warnings and Precautions (5.8)].

Hypothyroidism

Advise patients that RETEVMO can cause hypothyroidism and to immediately contact their healthcare provider for signs or symptoms of hypothyroidism [see Warnings and Precautions (5.9)].

Slipped Capital Femoral Epiphysis/Slipped Upper Femoral Epiphysis

Advise pediatric patients and caregivers to contact their healthcare provider promptly to report any signs and symptoms indicative of slipped capital femoral epiphysis/slipped upper femoral epiphysis [see Warnings and Precautions (5.11)].

Embryo-Fetal Toxicity

Advise pregnant women and females of reproductive potential of the possible risk to a fetus. Advise females of reproductive potential to inform their healthcare provider of a known or suspected pregnancy [see Warnings and Precautions (5.10), Use in Specific Populations (8.1)].

Advise females of reproductive potential to use effective contraception during the treatment with RETEVMO and for 1 week after the last dose [see Use in Specific Populations (8.3)].

Advise males with female partners of reproductive potential to use effective contraception during treatment with RETEVMO and for 1 week after the last dose [see Use in Specific Populations (8.3)].

Lactation

Advise women not to breastfeed during treatment with RETEVMO and for 1 week after the last dose [see Use in Specific Populations (8.2)].

Infertility

Advise males and females of reproductive potential that RETEVMO may impair fertility [see Use in Specific Populations (8.4), Nonclinical Toxicology (13.1)].

Drug Interactions

Advise patients and caregivers to inform their healthcare provider of all concomitant medications, including prescription medicines, over-the-counter drugs, vitamins, and herbal products. Inform patients to avoid St. John's wort, proton pump inhibitors, H2 receptor antagonists, and antacids while taking RETEVMO.

If PPIs are required, instruct patients to take RETEVMO with food. If H2 receptor antagonists are required, instruct patients to take RETEVMO 2 hours before or 10 hours after the H2 receptor antagonist. If locally-acting antacids are required, instruct patients to take RETEVMO 2 hours before or 2 hours after the locally-acting antacid [see Drug Interactions (7.1, 7.2)].

Marketed by: Lilly USA, LLC, Indianapolis, IN 46285, USA

Copyright © 2020, 2025, Eli Lilly and Company. All rights reserved.

Pat.: www.lilly.com/patents

RET-0009-USPI-20251120

PATIENT INFORMATION

RETEVMO® (reh-TEHV-moh)
(selpercatinib)
capsules

RETEVMO® (reh-TEHV-moh)
(selpercatinib)
tablets

What is RETEVMO?
RETEVMO is a prescription medicine that is used to treat certain cancers caused by abnormal RET genes in:

- adults with locally advanced non-small cell lung cancer (NSCLC) or NSCLC that has spread.
- adults and children 2 years of age and older with advanced medullary thyroid cancer (MTC) or MTC that has spread, who require a medicine by mouth or injection (systemic therapy).
- adults and children 2 years of age and older with advanced thyroid cancer or thyroid cancer that has spread who require a medicine by mouth or injection (systemic therapy), and who have received radioactive iodine and it did not work or is no longer working.
- adults and children 2 years of age and older with locally advanced solid tumors (cancers) or solid tumors that have spread, and have gotten worse (progressed) on or after other treatment or there are no satisfactory treatment options.

Your healthcare provider will perform a test to make sure that RETEVMO is right for you.
It is not known if RETEVMO is safe and effective when used:

- in children younger than 2 years of age for the treatment of:
  - advanced MTC or MTC that has spread who require a medicine by mouth or injection.
  - advanced thyroid cancer or thyroid cancer that has spread who require a medicine by mouth or injection, and have received radioactive iodine and it did not work or is no longer working.
  - locally advanced solid tumors or solid tumors that have spread, and have gotten worse on or after other treatment or there are no satisfactory treatment options.
- in children for other conditions.

Before taking RETEVMO, tell your healthcare provider about all your medical conditions, including if you:

- have liver problems
- have lung or breathing problems other than lung cancer
- have high blood pressure
- have heart problems including a condition called QT prolongation
- have bleeding problems
- plan to have surgery. You should stop taking RETEVMO at least 7 days before your planned surgery. See “What are the possible side effects of RETEVMO?”
- are pregnant or plan to become pregnant. RETEVMO can harm your unborn baby. You should not become pregnant during treatment with RETEVMO.
  - If you are able to become pregnant, your healthcare provider will do a pregnancy test before you start treatment with RETEVMO.
  - Females who are able to become pregnant should use effective birth control (contraception) during treatment and for 1 week after your last dose of RETEVMO. Talk to your healthcare provider about birth control methods that may be right for you.
  - Tell your healthcare provider right away if you become pregnant or think you might be pregnant during treatment with RETEVMO.
  - Males with female partners who are able to become pregnant should use effective birth control during treatment with RETEVMO and for 1 week after your last dose of RETEVMO.
- are breastfeeding or plan to breastfeed. It is not known if RETEVMO passes into your breast milk. Do not breastfeed during treatment with RETEVMO and for 1 week after your last dose.

Tell your healthcare provider about all the medicines you take, including prescription and over-the-counter medicines, vitamins, and herbal supplements. RETEVMO may affect the way other medicines work, and other medicines may affect how RETEVMO works, and may increase your risk of side effects.
During treatment with RETEVMO, you should avoid taking:

- St. John's wort
- proton pump inhibitors (PPIs), such as dexlansoprazole, esomeprazole, lansoprazole, omeprazole, pantoprazole sodium, and rabeprazole
- H2 blockers, such as famotidine, nizatidine, and cimetidine
- antacids that contain aluminum, magnesium, calcium, simethicone, or buffered medicines
- If you cannot avoid taking PPIs, H2 blockers, or antacids, see “How should I take RETEVMO?” for more information on how to take RETEVMO with these medicines.

Know the medicines you take. Keep a list of them to show your healthcare provider and pharmacist when you get a new medicine.

How should I take RETEVMO?

- Take RETEVMO exactly as your healthcare provider tells you.
- Your healthcare provider may change your dose, temporarily stop, or permanently stop treatment with RETEVMO if you have side effects. Do not change your dose or stop taking RETEVMO unless your healthcare provider tells you.
- Swallow RETEVMO capsules and tablets whole. Do not crush or chew.
- Do not take or give RETEVMO capsules or tablets if you or your child are unable to swallow.
  If you or your child are unable to swallow RETEVMO whole or if you or your child has a feeding tube, RETEVMO can be prepared and taken or given as a dispersion using only the RETEVMO 40 mg tablets. See the Instructions for Use that comes with RETEVMO for information about the right way to prepare and take or give a dose of RETEVMO 40 mg tablets.
- Take RETEVMO with or without food.
- If you take a proton-pump inhibitor (PPIs), such as dexlansoprazole, esomeprazole, lansoprazole, omeprazole, pantoprazole sodium, and rabeprazole, take RETEVMO with food.
- If you take an H2 blocker (such as famotidine, nizatidine, and cimetidine), take RETEVMO 2 hours before or 10 hours after taking the H2 blocker.
- If you take an antacid that contains aluminum, magnesium, calcium, simethicone, or buffered medicines, take RETEVMO 2 hours before or 2 hours after taking the antacid.
- If you vomit after taking a dose of RETEVMO, do not take an extra dose. Take the next dose of RETEVMO at your scheduled time.
- Do not take a missed dose of RETEVMO unless it is more than 6 hours until your next scheduled dose.

What are the possible side effects of RETEVMO?
RETEVMO may cause serious side effects, including:

- Liver problems. Liver problems (increased liver enzymes) can happen during treatment with RETEVMO and may sometimes be serious. Your healthcare provider will do blood tests before and during treatment with RETEVMO to check for liver problems. Tell your healthcare provider right away if you get any of the following symptoms of liver problems during treatment:
  - yellowing of your skin or the white part of your eyes (jaundice)
  - dark “tea-colored” urine
  - sleepiness
  - bleeding or bruising
  - loss of appetite
  - nausea or vomiting
  - pain on the upper right side of your stomach area
- Lung problems. RETEVMO may cause severe or life-threatening inflammation of the lungs during treatment, that can lead to death. Tell your healthcare provider right away if you have any new or worsening lung symptoms, including:
  - shortness of breath
  - cough
  - fever
- High blood pressure (hypertension). High blood pressure is common with RETEVMO and may sometimes be severe. You should check your blood pressure regularly during treatment with RETEVMO. If you develop blood pressure problems, your healthcare provider may prescribe medicine to treat your high blood pressure. Tell your healthcare provider if you have increased blood pressure readings or get any symptoms of high blood pressure, including:
  - confusion
  - headaches
  - shortness of breath
  - dizziness
  - chest pain
- Heart rhythm changes (QT prolongation). RETEVMO may cause very slow, very fast or irregular heartbeats. Your healthcare provider may perform tests before and during treatment with RETEVMO to check the activity of your heart and the levels of body salts (electrolytes) and thyroid-stimulating hormone (TSH) in your blood. Tell your healthcare provider right away if you get any of the following symptoms:
  - loss of consciousness
  - fainting
  - dizziness
  - a change in the way your heart beats (heart palpitations)
- Bleeding problems. RETEVMO can cause bleeding which can be serious and may lead to death. Tell your healthcare provider if you have any signs of bleeding during treatment with RETEVMO, including:
  - vomiting blood or if your vomit looks like coffee-grounds
  - pink or brown urine
  - red or black (looks like tar) stools
  - coughing up blood or blood clots
  - unusual bleeding or bruising of your skin
  - menstrual bleeding that is heavier than normal
  - unusual vaginal bleeding
  - nose bleeds that happen often
  - drowsiness or difficulty being awakened
  - confusion
  - headache
  - change in speech
- Allergic reactions. RETEVMO can cause a fever, rash, muscle or joint pain, especially during the first month of treatment. Tell your healthcare provider if you get any of these symptoms.
- Tumor lysis syndrome (TLS). TLS is caused by a fast breakdown of cancer cells. TLS can cause kidney failure, the need for dialysis treatment, and an abnormal heartbeat. TLS can lead to hospitalization. Your healthcare provider may do blood tests to check you for TLS. You should stay well hydrated during treatment with RETEVMO. Call your healthcare provider or get emergency medical help right away if you develop any of these symptoms during treatment with RETEVMO:
  - nausea
  - vomiting
  - weakness
  - swelling
  - shortness of breath
  - muscle cramps
  - seizures
- Risk of wound healing problems. Wounds may not heal properly during treatment with RETEVMO. Tell your healthcare provider if you plan to have any surgery before or during treatment with RETEVMO.
  - You should stop taking RETEVMO at least 7 days before planned surgery.
  - Your healthcare provider should tell you when you may start taking RETEVMO again after surgery.
- Low thyroid hormone levels in your blood (hypothyroidism). Your healthcare provider will do blood tests to check your thyroid function before and during treatment with RETEVMO. Tell your healthcare provider right away if you develop signs or symptoms of low thyroid hormone levels, including:
  - weight gain
  - feeling cold
  - tiredness that worsens or that does not go away
  - constipation
- Hip joint problems (slipped capital femoral epiphysis or slipped upper femoral epiphysis) in children. Tell your healthcare provider right away if you develop signs and symptoms of hip problems, including hip or knee pain or a painless limp.

The most common side effects of RETEVMO in adults with solid tumors include:

- swelling of your arms, legs, hands, and feet (edema)
- diarrhea
- tiredness
- dry mouth
- stomach-area (abdominal) pain

- constipation
- rash
- nausea
- headache

The most common side effects of RETEVMO in children 2 years and older with solid tumors include:

- muscle and bone pain
- diarrhea
- nausea
- bleeding
- fever
- stomach-area (abdominal) pain
- headache

- vomiting
- tiredness
- cough
- rash
- coronavirus infection
- upper respiratory tract infection
- swelling

The most common severe abnormal laboratory test results with RETEVMO in adults with solid tumors include decreased white blood cell count, increased liver enzymes, decreased levels of sodium in the blood, and decreased levels of calcium in the blood.
The most common severe abnormal laboratory test results with RETEVMO in children 2 years and older with solid tumors include decreased white blood cell count, decreased levels of calcium in the blood, decreased red blood cell count, increased liver enzymes, decreased levels of magnesium in the blood, and decreased levels of potassium in the blood.
RETEVMO may affect fertility in females and males, which may affect your ability to have children. Talk to your healthcare provider if this is a concern for you.
These are not all the possible side effects with RETEVMO.
Call your doctor for medical advice about side effects. You may report side effects to FDA at 1-800-FDA-1088.

How should I store RETEVMO?

- Store RETEVMO at room temperature between 68°F to 77°F (20°C to 25°C).

Keep RETEVMO and all medicines out of the reach of children.

General information about the safe and effective use of RETEVMO.
Medicines are sometimes prescribed for purposes other than those listed in a Patient Information leaflet. Do not use RETEVMO for a condition for which it was not prescribed. Do not give RETEVMO to other people, even if they have the same symptoms you have. It may harm them. You can ask your pharmacist or healthcare provider for more information about RETEVMO that is written for health professionals.

What are the ingredients in RETEVMO?
Active ingredient: selpercatinib
Capsules: colloidal silicon dioxide and microcrystalline cellulose. The 40 mg capsule shell contains: gelatin, titanium dioxide, ferric oxide black and black ink. The 80 mg capsule shell contains: gelatin, titanium dioxide, FD&C blue #1 and black ink. The black ink contains: shellac, potassium hydroxide and ferric oxide black.
Tablets: croscarmellose sodium, hydroxypropyl cellulose, mannitol, microcrystalline cellulose, and sodium stearyl fumarate. The tablet film coating material contains polyvinyl alcohol, titanium dioxide, polyethylene glycol, and talc. Additionally, the film coating of the 40 mg, 80 mg, and 120 mg tablets contains ferrosoferric oxide and the film coating of the 80 mg, 120 mg, and 160 mg tablets contain ferric oxide.
Marketed by: Lilly USA, LLC, Indianapolis, IN 46285, USA
Copyright © 2020, 2025, Eli Lilly and Company. All rights reserved.
RET-0008-PPI-20251120

This Patient Information has been approved by the U.S. Food and Drug Administration.

Revised:11/2025

INSTRUCTIONS FOR USE

RETEVMO® (reh-TEHV-moh)
(selpercatinib)
tablets

This Instructions for Use contains information on how to prepare and take or give a dose of RETEVMO tablets if you cannot swallow the tablet whole or if you have a feeding tube. Read this Instructions for Use before you prepare and take or give RETEVMO and each time you get a refill. This information does not take the place of talking to your healthcare provider about your medical condition or treatment. Talk to your healthcare provider or pharmacist if you have any questions.
Important Information You Need to Know Before Preparing a dose of RETEVMO:

- Use only RETEVMO 40 mg tablets to make the dispersion. RETEVMO 40 mg tablets are light gray, film coated, round tablets with “Ret 40” on one side and “5340” on the other side.
  Prescribed Dose | Number of 40 mg tablets
  40 mg | 1
  80 mg | 2
  120 mg | 3
  160 mg | 4

Preparing and taking or giving RETEVMO
Gather the following supplies:

- the number of RETEVMO 40 mg tablet(s) needed for your prescribed dose
- water (room temperature or chilled) or 100% carrot puree
- an empty glass or medicine cup
- a spoon

Step 1 Add about 1 tablespoon (15 mL) of room temperature or chilled water or 100% carrot puree to a glass or medicine cup.
Step 2 Place the prescribed number of 40 mg tablet(s) in the glass or medicine cup.
Step 3 Stir the tablet(s) in the water or carrot puree until the tablet(s) have dispersed (evenly mixed). It will take about 7 to 10 minutes for the tablet(s) to fully disperse. The tablet(s) mixture may be cloudy if water is used.
Step 4 Take or give all of the tablet(s) mixture right away.
Step 5 There will be some tablet(s) mixture remaining in the glass or medicine cup. Add 1 tablespoon (15 mL) of water or carrot puree to the same glass or medicine cup and swirl or stir to mix any remaining tablet(s) mixture. Drink the tablet(s) mixture right away.
Step 6 Repeat Step 5, as necessary, to make sure the entire dose is taken or given.
Step 7 Wash your hands and all supplies used with warm soapy water.
If the RETEVMO tablet(s) mixture is not taken within 2 hours after it is prepared, throw it away in your household trash.

Preparing and taking or giving RETEVMO through a feeding tube (gastrostomy or nasogastric tube):
RETEVEMO tablets can be given through a gastrostomy or nasogastric tube according to the manufacturer's instructions and as directed by your healthcare provider. Use only polyurethane (French size 8 or larger) or vinyl chloride (French size 10 or larger) nasogastric tubes or silicone (French size 14 or larger) gastrostomy tubes.
Gather the following supplies:

- the number of RETEVMO 40 mg tablet(s) needed for your prescribed dose
- room temperature water
- an empty glass or medicine cup
- a spoon
- an enteral syringe

Ask your pharmacist for an enteral syringe if you do not have one.
Step 1 Add at least 10 mL of room temperature water to a glass or medicine cup.
Step 2 Place the prescribed number of 40 mg tablet(s) in the glass or cup.
Step 3 Stir the tablet(s) in the water until the tablet(s) have dispersed (evenly mixed). It will take about 7 to 10 minutes for the tablets to fully disperse. The tablet(s) mixture may be cloudy.
Step 4 Flush the feeding tube according to the manufacturer's instructions.
Step 5 Draw up all of the tablet(s) mixture from the glass or medicine cup into an enteral syringe. Attach the enteral syringe tip into the feeding tube and give the tablet(s) mixture right away.
Step 6 There will be some tablet(s) mixture remaining in the glass or medicine cup. Add 5 mL of water to the same glass or medicine cup and swirl or stir to mix any remaining tablet(s) mixture. Draw up all of the tablet(s) mixture into the same enteral syringe and give it through the feeding tube right away.
Step 7 Repeat Step 6, as necessary, to make sure the entire dose is given.
Step 8 Flush the feeding tube according to the manufacturer's instructions.
Step 9 Wash your hands and all supplies used with warm soapy water. Follow the manufacturer's instructions to clean the enteral syringe.
If the RETEVMO tablet(s) mixture is not given within 2 hours after it is prepared, throw it away in your household trash.

Storing RETEVMO Tablets

- Store RETEVMO at room temperature between 68°F to 77°F (20°C to 25°C).

Keep RETEVMO and all medicines out of the reach of children.
Marketed by: Lilly USA, LLC, Indianapolis, IN 46285, USA
Copyright © 2025 Eli Lilly and Company. All rights reserved.
RET-0001-IFU-20251120

This Instruction for Use has been approved by the U.S. Food and Drug Administration.

Approved:11/2025

PACKAGE LABEL - Retevmo 40 mg Capsules

NDC-0002-3977-60

60 capsules

Rx only

Retevmo®

(selpercatinib)

capsules

40 mg

Each capsule contains
40 mg selpercatinib

www.retevmo.com

Lilly

PACKAGE LABEL - Retevmo 80 mg Capsules

NDC-0002-2980-60

60 capsules

Rx only

Retevmo®

(selpercatinib)

capsules

80 mg

Each capsule contains
80 mg selpercatinib

www.retevmo.com

Lilly

PACKAGE LABEL – Retevmo 40mg Tablets

NDC 0002-5340-60

60 tablets Rx only

Retevmo®

(selpercatinib)
tablets

40 mg

Each tablet contains 40 mg selpercatinib

www.retevmo.com

Lilly

PACKAGE LABEL – Retevmo 80mg Tablets

NDC 0002-6082-60

60 tablets Rx only

Retevmo®

(selpercatinib)
tablets

80 mg

Each tablet contains 80 mg selpercatinib

www.retevmo.com

Lilly

PACKAGE LABEL – Retevmo 120mg Tablets

NDC 0002-6120-60

60 tablets Rx only

Retevmo®

(selpercatinib)
tablets

120 mg

Each tablet contains 120 mg selpercatinib

www.retevmo.com

Lilly

PACKAGE LABEL – Retevmo 160mg Tablets

NDC 0002-5562-60

60 tablets Rx only

Retevmo®

(selpercatinib)
tablets

160 mg

Each tablet contains 160 mg selpercatinib

www.retevmo.com

Lilly